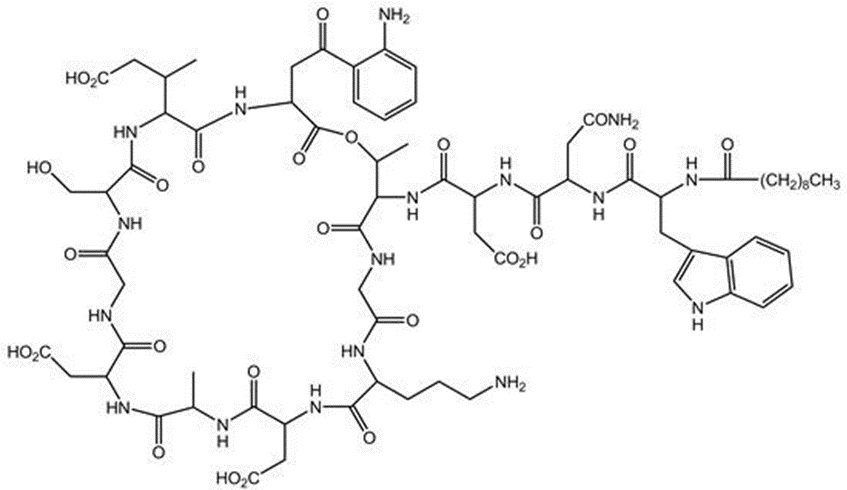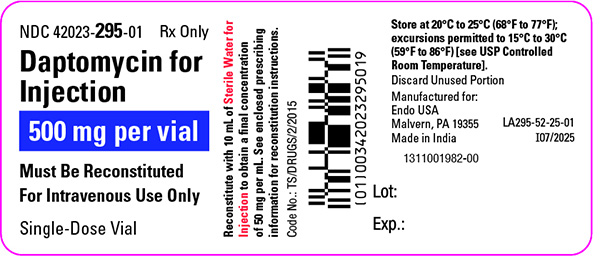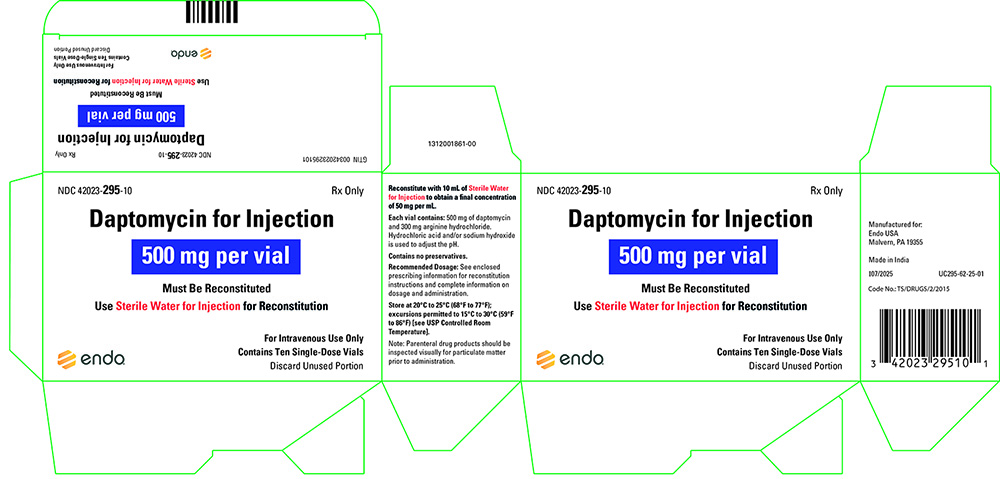 DRUG LABEL: Daptomycin
NDC: 42023-295 | Form: INJECTION, POWDER, LYOPHILIZED, FOR SOLUTION
Manufacturer: Par Health USA, LLC
Category: prescription | Type: HUMAN PRESCRIPTION DRUG LABEL
Date: 20250819

ACTIVE INGREDIENTS: DAPTOMYCIN 500 mg/1 1
INACTIVE INGREDIENTS: ARGININE HYDROCHLORIDE 300 mg/1 1; SODIUM HYDROXIDE; HYDROCHLORIC ACID

HIGHLIGHTS OF PRESCRIBING INFORMATION

These highlights do not include all the information needed to use DAPTOMYCIN FOR INJECTION safely and effectively. See full prescribing information for DAPTOMYCIN FOR INJECTION.
DAPTOMYCIN for injection, for intravenous use
Initial U.S. Approval: 2003

1 INDICATIONS AND USAGE

Daptomycin for Injection is a lipopeptide antibacterial indicated for the treatment of:
• Complicated skin and skin structure infections (cSSSI) in adult and pediatric patients (1 to 17 years of age) (1.1) and,
• Staphylococcus aureus bloodstream infections (bacteremia), in adult patients including those with right-sided infective endocarditis, (1.2)
• Staphylococcus aureus bloodstream infections (bacteremia) in pediatric patients (1 to 17 years of age). (1.3)

Limitations of Use:
• Daptomycin for Injection is not indicated for the treatment of pneumonia. (1.4)
• Daptomycin for Injection is not indicated for the treatment of left-sided infective endocarditis due to S. aureus. (1.4)
• Daptomycin for Injection is not recommended in pediatric patients younger than one year of age due to the risk of potential effects on muscular, neuromuscular, and/or nervous systems (either peripheral and/or central) observed in neonatal dogs. (1.4)

To reduce the development of drug-resistant bacteria and maintain the effectiveness of Daptomycin for Injection and other antibacterial drugs, Daptomycin for Injection should be used to treat or prevent infections that are proven or strongly suspected to be caused by bacteria. (1.5)

2 DOSAGE AND ADMINISTRATION

Adult Patients
• Administer to adult patients intravenously, either by injection over a 2-minute period or by infusion over a 30-minute period. (2.1, 2.7)
• Recommended dosage regimen for adult patients (2.2, 2.4, 2.6):

Creatinine Clearance (CLCR) | Dosage Regimen
Creatinine Clearance (CLCR) | cSSSI For 7 to 14 days | S. aureus Bacteremia For 2 to 6 weeks
≥30 mL/min | 4 mg/kg once every 24 hours | 6 mg/kg once every 24 hours
<30 mL/min, including hemodialysis and CAPD | 4 mg/kg once every 48 hours* | 6 mg/kg once every 48 hours*
* Administered following hemodialysis on hemodialysis days.

Pediatric Patients
• Unlike in adults, do NOT administer by injection over a two (2) minute period to pediatric patients. (2.1, 2.7)
• Administer to pediatric patients intravenously by infusion over a 30- or 60-minute period, based on age. (2.1, 2.7)
• Recommended dosage regimen for pediatric patients (1 to 17 years of age) with cSSSI, based on age (2.3):

Age Group | Dosage* | Duration of therapy
12 to 17 years | 5 mg/kg once every 24 hours infused over 30 minutes | Up to 14 days
7 to 11 years | 7 mg/kg once every 24 hours infused over 30 minutes | Up to 14 days
2 to 6 years | 9 mg/kg once every 24 hours infused over 60 minutes | Up to 14 days
1 to less than 2 years | 10 mg/kg once every 24 hours infused over 60 minutes | Up to 14 days
*Recommended dosage is for pediatric patients (1 to 17 years of age) with normal renal function. Dosage adjustment for pediatric patients with renal impairment has not been established.

• Recommended dosage regimen for pediatric patients (1 to 17 years of age) with S. aureus bacteremia, based on age (2.5):

Age Group | Dosage* | Duration of therapy
12 to 17 years | 7 mg/kg once every 24 hours infused over 30 minutes | Up to 42 days
7 to 11 years | 9 mg/kg once every 24 hours infused over 30 minutes | Up to 42 days
1 to 6 years | 12 mg/kg once every 24 hours infused over 60 minutes | Up to 42 days
*Recommended dosage is for pediatric patients (1 to 17 years of age) with normal renal function. Dosage adjustment for pediatric patients with renal impairment has not been established.

• There are other formulations of daptomycin that have differences concerning storage and reconstitution. Carefully follow the reconstitution and storage procedures in labeling. (2.7)

• Do not use in conjunction with ReadyMED® elastomeric infusion pumps in adult and pediatric patients. (2.9)

3 DOSAGE FORMS AND STRENGTHS

• For Injection: 350 mg of daptomycin as a lyophilized powder in a single-dose vial for reconstitution (3)
• For Injection: 500 mg of daptomycin as a lyophilized powder in a single-dose vial for reconstitution (3)

4 CONTRAINDICATIONS

- Known hypersensitivity to daptomycin (4)

5 WARNINGS AND PRECAUTIONS

• Anaphylaxis/hypersensitivity reactions (including life-threatening): Discontinue Daptomycin for Injection and treat signs/symptoms. (5.1)
• Myopathy and rhabdomyolysis: Monitor CPK levels and follow muscle pain or weakness; if elevated CPK or myopathy occurs, consider discontinuation of Daptomycin for Injection. (5.2)
• Eosinophilic pneumonia: Discontinue Daptomycin for Injection and consider treatment with systemic steroids. (5.3)
• Drug Reaction with Eosinophilia and Systemic Symptoms (DRESS): Discontinue daptomycin and institute appropriate treatment. (5.4)
• Tubulointerstitial Nephritis (TIN): Discontinue Daptomycin for Injection and institute appropriate treatment. (5.5)
• Peripheral neuropathy: Monitor for neuropathy and consider discontinuation. (5.6)
• Potential nervous system and/or muscular system effects in pediatric patients younger than 12 months: Avoid use of Daptomycin for Injection in this age group. (5.7)
• Clostridioides difficile-associated diarrhea: Evaluate patients if diarrhea occurs. (5.8)
• Persisting or relapsing S. aureus bacteremia/endocarditis: Perform susceptibility testing and rule out sequestered foci of infection. (5.9)
• Decreased efficacy was observed in adult patients with moderate baseline renal impairment. (5.10)

6 ADVERSE REACTIONS

• Adult cSSSI Patients: The most common adverse reactions that occurred in ≥2% of adult cSSSI patients receiving daptomycin for injection 4 mg/kg were diarrhea, headache, dizziness, rash, abnormal liver function tests, elevated creatine phosphokinase (CPK), urinary tract infections, hypotension, and dyspnea. (6.1)
• Pediatric cSSSI Patients: The most common adverse reactions that occurred in ≥2% of pediatric patients receiving daptomycin for injection were diarrhea, vomiting, abdominal pain, pruritus, pyrexia, elevated CPK, and headache. (6.1)
• Adult S. aureus bacteremia/endocarditis Patients: The most common adverse reactions that occurred in ≥5% of S. aureus bacteremia/endocarditis patients receiving daptomycin for injection 6 mg/kg were sepsis, bacteremia, abdominal pain, chest pain, edema, pharyngolaryngeal pain, pruritus, increased sweating, insomnia, elevated CPK, and hypertension. (6.1)
• Pediatric S. aureus bacteremia Patients: The most common adverse reactions that occurred in ≥5% of pediatric patients receiving daptomycin for injection were vomiting and elevated CPK. (6.1)

To report SUSPECTED ADVERSE REACTIONS, contact Endo at 1-800-828-9393 or FDA at 1-800-FDA-1088 or www.fda.gov/medwatch.

FULL PRESCRIBING INFORMATION

1 INDICATIONS AND USAGE

1.1 Complicated Skin and Skin Structure Infections (cSSSI)

Daptomycin for Injection is indicated for the treatment of adult and pediatric patients (1 to 17 years of age) with complicated skin and skin structure infections (cSSSI) caused by susceptible isolates of the following Gram-positive bacteria: Staphylococcus aureus (including methicillin-resistant isolates), Streptococcus pyogenes, Streptococcus agalactiae, Streptococcus dysgalactiae subsp. equisimilis, and Enterococcus faecalis (vancomycin-susceptible isolates only).

1.2 Staphylococcus aureus Bloodstream Infections (Bacteremia) in Adult Patients, Including Those with Right-Sided Infective Endocarditis, Caused by Methicillin-Susceptible and Methicillin-Resistant Isolates

Daptomycin for Injection is indicated for the treatment of adult patients with Staphylococcus aureus bloodstream infections (bacteremia), including adult patients with right-sided infective endocarditis, caused by methicillin-susceptible and methicillin-resistant isolates.

1.3 Staphylococcus aureus Bloodstream Infections (Bacteremia) in Pediatric Patients (1 to 17 Years of Age)

Daptomycin for Injection is indicated for the treatment of pediatric patients (1 to 17 years of age) with Staphylococcus aureus bloodstream infections (bacteremia)

1.4 Limitations of Use

Daptomycin for Injection is not indicated for the treatment of pneumonia.

Daptomycin for Injection is not indicated for the treatment of left-sided infective endocarditis due to S. aureus. The clinical trial of Daptomycin for Injection in adult patients with S. aureus bloodstream infections included limited data from patients with left-sided infective endocarditis; outcomes in these patients were poor [see Clinical Studies (14.2)]. Daptomycin for Injection has not been studied in patients with prosthetic valve endocarditis.

Daptomycin for Injection is not recommended in pediatric patients younger than 1 year of age due to the risk of potential effects on muscular, neuromuscular, and/or nervous systems (either peripheral and/or central) observed in neonatal dogs [see Warnings and Precautions (5.7) and Nonclinical Toxicology (13.2)].

1.5 Usage

Appropriate specimens for microbiological examination should be obtained in order to isolate and identify the causative pathogens and to determine their susceptibility to daptomycin.

To reduce the development of drug-resistant bacteria and maintain the effectiveness of Daptomycin for Injection and other antibacterial drugs, Daptomycin for Injection should be used only to treat or prevent infections that are proven or strongly suspected to be caused by susceptible bacteria.

When culture and susceptibility information is available, it should be considered in selecting or modifying antibacterial therapy. In the absence of such data, local epidemiology and susceptibility patterns may contribute to the empiric selection of therapy. Empiric therapy may be initiated while awaiting test results.

2 DOSAGE AND ADMINISTRATION

2.1 Important Administration Duration Instructions

Adults
Administer the appropriate volume of the reconstituted Daptomycin for Injection (concentration of 50 mg/mL) to adult patients intravenously either by injection over a two (2) minute period or by intravenous infusion over a thirty (30) minute period [see Dosage and Administration (2.2, 2.4, 2.7)].

Pediatric Patients (1 to 17 Years of Age)
Unlike in adults, do NOT administer Daptomycin for Injection by injection over a two (2) minute period to pediatric patients.

- Pediatric Patients 7 to 17 years of Age: Administer Daptomycin for Injection intravenously by infusion over a 30-minute period [see Dosage and Administration (2.3, 2.5, 2.7)].
- Pediatric Patients 1 to 6 years of Age: Administer Daptomycin for Injection intravenously by infusion over a 60-minute period [see Dosage and Administration (2.3, 2.5, 2.7)].

2.2 Dosage in Adults for cSSSI

Administer Daptomycin for Injection 4 mg/kg to adult patients intravenously once every 24 hours for 7 to 14 days.

2.3 Dosage in Pediatric Patients (1 to 17 Years of Age) for cSSSI

The recommended dosage regimens based on age for pediatric patients with cSSSI are shown in Table 1. Administer Daptomycin for Injection intravenously once every 24 hours for up to 14 days.

Table 1: Recommended Dosage of Daptomycin for Injection in Pediatric Patients (1 to 17 Years of Age) with cSSSI, Based on Age

Age Range | Dosage Regimen* | Duration of therapy
12 to 17 years | 5 mg/kg once every 24 hours infused over 30 minutes | Up to 14 days
7 to 11 years | 7 mg/kg once every 24 hours infused over 30 minutes | Up to 14 days
2 to 6 years | 9 mg/kg once every 24 hours infused over 60 minutes | Up to 14 days
1 to less than 2 years | 10 mg/kg once every 24 hours infused over 60 minutes | Up to 14 days
* Recommended dosage regimen is for pediatric patients (1 to 17 years of age) with normal renal function. Dosage adjustment for pediatric patients with renal impairment has not been established.

2.4 Dosage in Adult Patients with Staphylococcus aureus Bloodstream Infections (Bacteremia), Including Those with Right-Sided Infective Endocarditis, Caused by Methicillin-Susceptible and Methicillin-Resistant Isolates

Administer Daptomycin for Injection 6 mg/kg to adult patients intravenously once every 24 hours for 2 to 6 weeks. There are limited safety data for the use of Daptomycin for Injection for more than 28 days of therapy. In the Phase 3 trial, there were a total of 14 adult patients who were treated with Daptomycin for Injection for more than 28 days.

2.5 Dosage in Pediatric Patients (1 to 17 Years of Age) with Staphylococcus aureus Bloodstream Infections (Bacteremia)

The recommended dosage regimens based on age for pediatric patients with S. aureus bloodstream infections (bacteremia) are shown in Table 2. Administer Daptomycin for Injection intravenously in 0.9% sodium chloride injection once every 24 hours for up to 42 days.

Table 2: Recommended Dosage of Daptomycin for Injection in Pediatric Patients (1 to 17 Years of Age) with S. aureus Bacteremia, Based on Age

Age Group | Dosage* | Duration of therapy
12 to 17 years | 7 mg/kg once every 24 hours infused over 30 minutes | Up to 42 days
7 to 11 years | 9 mg/kg once every 24 hours infused over 30 minutes | Up to 42 days
1 to 6 years | 12 mg/kg once every 24 hours infused over 60 minutes | Up to 42 days
* Recommended dosage is for pediatric patients (1 to 17 years of age) with normal renal function. Dosage adjustment for pediatric patients with renal impairment has not been established.

2.6 Dosage in Patients with Renal Impairment

Adult Patients:
No dosage adjustment is required in adult patients with creatinine clearance (CLCR) greater than or equal to 30 mL/min. The recommended dosage regimen for Daptomycin for Injection in adult patients with CLCR less than 30 mL/min, including adult patients on hemodialysis or continuous ambulatory peritoneal dialysis (CAPD), is 4 mg/kg (cSSSI) or 6 mg/kg (S. aureus bloodstream infections) once every 48 hours (Table 3). When possible, Daptomycin for Injection should be administered following the completion of hemodialysis, on hemodialysis days [see Warnings and Precautions (5.2, 5.10), Use in Specific Populations (8.6), and Clinical Pharmacology (12.3)].

Table 3: Recommended Dosage of Daptomycin for Injection in Adult Patients

Creatinine Clearance (CLCR) | Dosage Regimen in Adults
Creatinine Clearance (CLCR) | cSSSI | S. aureus Bloodstream Infections
Greater than or equal to 30 mL/min | 4 mg/kg once every 24 hours | 6 mg/kg once every 24 hours
Less than 30 mL/min, including hemodialysis and CAPD | 4 mg/kg once every 48 hours* | 6 mg/kg once every 48 hours*

* When possible, administer Daptomycin for Injection following the completion of hemodialysis, on hemodialysis days.

Pediatric Patients:
The dosage regimen for Daptomycin for Injection in pediatric patients with renal impairment has not been established.

2.7 Preparation and Administration of Daptomycin for Injection

There are other formulations of daptomycin that have differences concerning reconstitution and storage. Carefully follow the reconstitution and storage procedures described in this labeling.

Reconstitution of Daptomycin for Injection Vial

Daptomycin for Injection must be reconstituted within the vial only with Sterile Water for Injection. Do NOT use saline based diluents for the reconstitution in the vial because this will result in a hyperosmotic solution that may result in injection site reactions if the reconstituted product is administered as an intravenous injection over a period of 2 minutes.

Reconstitution Procedure
Daptomycin for Injection is supplied in single-dose vials, each containing 350 mg or 500 mg daptomycin as a sterile, lyophilized powder. The contents of a Daptomycin for Injection vial should be reconstituted, using aseptic technique, to 50 mg/mL as follows:

1. To minimize foaming, AVOID vigorous agitation or shaking of the vial during or after reconstitution.
2. Remove the polypropylene flip-off cap from the Daptomycin for Injection vial to expose the central portion of the rubber stopper.
3. Wipe the top of the rubber stopper with an alcohol swab or other antiseptic solution and allow to dry. After cleaning, do not touch the rubber stopper or allow it to touch any other surface.
4. Slowly transfer 7 mL (for 350 mg/vial) or 10 mL (for 500 mg/vial) of the recommended reconstitution fluid through the center of the rubber stopper into the Daptomycin for Injection vial, pointing the transfer needle toward the wall of the vial. Use a beveled sterile transfer needle that is 21 gauge or smaller in diameter, pointing the transfer needle toward the wall of the vial.
5. Ensure that all of the Daptomycin for Injection powder is wetted by holding the vial upright by the cap and gently swirling in a circular motion or gently rotating from upright to horizontal orientation for a few minutes, as needed, to obtain a completely reconstituted solution.

Administration Instructions

Parenteral drug products should be inspected visually for particulate matter prior to administration.
Slowly remove reconstituted liquid (50 mg daptomycin/mL) from the vial using a beveled sterile needle that is 21 gauge or smaller in diameter. Administer as an intravenous injection or infusion as described below:

Adults
Intravenous Injection over a period of 2 minutes
• For intravenous (IV) injection over a period of 2 minutes in adult patients only: Administer the appropriate volume of the reconstituted Daptomycin for Injection (concentration of 50 mg/mL).
Intravenous Infusion over a period of 30 minutes
• For IV infusion over a period of 30 minutes in adult patients: The appropriate volume of the reconstituted Daptomycin for Injection (concentration of 50 mg/mL) should be further diluted, using aseptic technique, into a 50 mL IV infusion bag containing 0.9% sodium chloride injection or Lactated Ringer’s Injection.

Pediatric Patients (1 to 17 Years of Age)
Intravenous Infusion over a period of 30 or 60 minutes
• Unlike in Adults, do NOT administer Daptomycin for Injection by injection over a two (2) minute period to pediatric patients [see Dosage and Administration (2.1)].
• For Intravenous infusion over a period of 60 minutes in pediatric patients 1 to 6 years of age: The appropriate volume of the reconstituted Daptomycin for Injection (concentration of 50 mg/mL) should be further diluted, using aseptic technique, into an intravenous infusion bag containing 25 mL of 0.9% sodium chloride injection or Lactated Ringer’s Injection. The infusion rate should be maintained at 0.42 mL/minute over the 60-minute period.
• For Intravenous infusion over a period of 30 minutes in pediatric patients 7 to 17 years of age: The appropriate volume of the Daptomycin for Injection reconstituted in either Sterile Water for Injection or 0.9% sodium chloride injection (concentration of 50 mg/mL) should be further diluted, using aseptic technique, into a 50 mL IV infusion bag containing 0.9% sodium chloride injection or Lactated Ringer’s. The infusion rate should be maintained at 1.67 mL/minute over the 30-minute period.

No preservative or bacteriostatic agent is present in this product. Aseptic technique must be used in the preparation of final IV solution. Table 4 below provides in-use storage conditions for reconstituted Daptomycin for Injection in acceptable intravenous diluents in the syringe, vial and intravenous bag (for reconstitution and dilution). Do not exceed the listed shelf-life of reconstituted and diluted solutions of Daptomycin for Injection. Discard unused portions of Daptomycin for Injection.

Table 4: In-Use Storage Conditions for Daptomycin for Injection Once Reconstituted with Sterile Water for Injection

Container | Diluent | In-Use Shelf-Life
Container | Diluent | Room Temperature (20°C–25°C, 68°F–77°F) | Refrigerated (2°C–8°C, 36°F–46°F)
Vial | Sterile Water for Injection | 18 Hours | 5 Days
Syringe* | Sterile Water for Injection | 18 Hours | 10 Days
Intravenous Bag | Vial reconstituted with Sterile Water for Injection and immediately diluted with 0.9% sodium chloride injection | 18 Hours | 10 Days
Intravenous Bag | Vial reconstituted with Sterile Water for Injection and immediately diluted with Lactated Ringer’s injection. | 18 Hours | 2 Days

* Polypropylene syringe with elastomeric plunger stopper.

2.8 Compatible Intravenous Solution for Reconstitution and Dilution

Daptomycin for Injection is compatible with Sterile Water for Injection for reconstitution. [see Dosage and Administration (2.7)].
Reconstituted Daptomycin for Injection can be diluted with 0.9% sodium chloride injection or Lactated Ringer’s injection.

2.9 Incompatibilities

Daptomycin for Injection is not compatible with dextrose-containing diluents.

Daptomycin for Injection should not be used in conjunction with ReadyMED® elastomeric infusion pumps. Stability studies of Daptomycin for Injection solutions stored in ReadyMED® elastomeric infusion pumps identified an impurity (2-mercaptobenzothiazole) leaching from this pump system into the Daptomycin for Injection solution.

Because only limited data are available on the compatibility of Daptomycin for Injection with other IV substances, additives and other medications should not be added to Daptomycin for Injection single-dose vials or infusion bags, or infused simultaneously with Daptomycin for Injection through the same IV line. If the same IV line is used for sequential infusion of different drugs, the line should be flushed with a compatible intravenous solution before and after infusion with Daptomycin for Injection.

3 DOSAGE FORMS AND STRENGTHS

For Injection: 350 mg or 500 mg daptomycin as a sterile, pale yellow to light brown lyophilized powder for reconstitution in a single-dose vial.

4 CONTRAINDICATIONS

Daptomycin for Injection is contraindicated in patients with known hypersensitivity to daptomycin [see Warnings and Precautions (5.1)].

5 WARNINGS AND PRECAUTIONS

5.1 Anaphylaxis/Hypersensitivity Reactions

Anaphylaxis/hypersensitivity reactions have been reported with the use of antibacterial agents, including daptomycin for injection, and may be life-threatening. If an allergic reaction to Daptomycin for Injection occurs, discontinue the drug and institute appropriate therapy [see Adverse Reactions (6.2)].

5.2 Myopathy and Rhabdomyolysis

Myopathy, defined as muscle aching or muscle weakness in conjunction with increases in creatine phosphokinase (CPK) values to greater than 10 times the upper limit of normal (ULN), has been reported with the use of daptomycin. Rhabdomyolysis, with or without acute renal failure, has been reported [see Adverse Reactions (6.2)].
Patients receiving Daptomycin for Injection should be monitored for the development of muscle pain or weakness, particularly of the distal extremities. In patients who receive Daptomycin for Injection, CPK levels should be monitored weekly, and more frequently in patients who received recent prior or concomitant therapy with an HMG-CoA reductase inhibitor or in whom elevations in CPK occur during treatment with Daptomycin for Injection.
In adult patients with renal impairment, both renal function and CPK should be monitored more frequently than once weekly [see Use in Specific Populations (8.6) and Clinical Pharmacology (12.3)].
In Phase 1 studies and Phase 2 clinical trials in adults, CPK elevations appeared to be more frequent when Daptomycin for Injection was dosed more than once daily. Therefore, Daptomycin for Injection should not be dosed more frequently than once a day.
Daptomycin for Injection should be discontinued in patients with unexplained signs and symptoms of myopathy in conjunction with CPK elevations to levels >1,000 U/L (~5× ULN), and in patients without reported symptoms who have marked elevations in CPK, with levels >2,000 U/L (≥10× ULN).
In addition, consideration should be given to suspending agents associated with rhabdomyolysis, such as HMG-CoA reductase inhibitors, temporarily in patients receiving daptomycin [see Drug Interactions (7.1)].

5.3 Eosinophilic Pneumonia

Eosinophilic pneumonia has been reported in patients receiving daptomycin for injection [see Adverse Reactions (6.2)]. In reported cases associated with daptomycin for injection, patients developed fever, dyspnea with hypoxic respiratory insufficiency, and diffuse pulmonary infiltrates or organizing pneumonia. In general, patients developed eosinophilic pneumonia 2 to 4 weeks after starting daptomycin for injection and improved when daptomycin for injection was discontinued and steroid therapy was initiated. Recurrence of eosinophilic pneumonia upon re-exposure has been reported. Patients who develop these signs and symptoms while receiving Daptomycin for Injection should undergo prompt medical evaluation, and Daptomycin for Injection should be discontinued immediately. Treatment with systemic steroids is recommended.

5.4 Drug Reaction with Eosinophilia and Systemic Symptoms (DRESS)

DRESS has been reported in post-marketing experience with daptomycin for injection [see Adverse Reactions (6.2)]. Patients who develop skin rash, fever, peripheral eosinophilia, and systemic organ (for example, hepatic, renal, pulmonary) impairment while receiving Daptomycin for Injection should undergo medical evaluation. If DRESS is suspected, discontinue Daptomycin for Injection promptly and institute appropriate treatment.

5.5 Tubulointerstitial Nephritis (TIN)

TIN has been reported in post-marketing experience with daptomycin for injection [see Adverse Reactions (6.2)]. Patients who develop new or worsening renal impairment while receiving Daptomycin for Injection should undergo medical evaluation. If TIN is suspected, discontinue Daptomycin for Injection promptly and institute appropriate treatment.

5.6 Peripheral Neuropathy

Cases of peripheral neuropathy have been reported during the daptomycin postmarketing experience [see Adverse Reactions (6.2)]. Therefore, physicians should be alert to signs and symptoms of peripheral neuropathy in patients receiving daptomycin. Monitor for neuropathy and consider discontinuation.

5.7 Potential Nervous System and/or Muscular System Effects in Pediatric Patients Younger than 12 Months

Avoid use of Daptomycin for Injection in pediatric patients younger than 12 months due to the risk of potential effects on muscular, neuromuscular, and/or nervous systems (either peripheral and/or central) observed in neonatal dogs with intravenous daptomycin [see Nonclinical Toxicology (13.2)].

5.8 Clostridioides difficile-Associated Diarrhea

Clostridioides difficile-associated diarrhea (CDAD) has been reported with the use of nearly all systemic antibacterial agents, including daptomycin for injection, and may range in severity from mild diarrhea to fatal colitis [see Adverse Reactions (6.2)]. Treatment with antibacterial agents alters the normal flora of the colon, leading to overgrowth of C. difficile.
C. difficile produces toxins A and B, which contribute to the development of CDAD. Hypertoxin-producing strains of C. difficile cause increased morbidity and mortality, since these infections can be refractory to antimicrobial therapy and may require colectomy. CDAD must be considered in all patients who present with diarrhea following antibacterial use. Careful medical history is necessary because CDAD has been reported to occur more than 2 months after the administration of antibacterial agents.
If CDAD is suspected or confirmed, ongoing antibacterial use not directed against C. difficile may need to be discontinued. Appropriate fluid and electrolyte management, protein supplementation, antibacterial treatment of C. difficile, and surgical evaluation should be instituted as clinically indicated.

5.9 Persisting or Relapsing S. aureus Bacteremia/Endocarditis

Patients with persisting or relapsing S. aureus bacteremia/endocarditis or poor clinical response should have repeat blood cultures. If a blood culture is positive for S. aureus, minimum inhibitory concentration (MIC) susceptibility testing of the isolate should be performed using a standardized procedure, and diagnostic evaluation of the patient should be performed to rule out sequestered foci of infection. Appropriate surgical intervention (e.g., debridement, removal of prosthetic devices, valve replacement surgery) and/or consideration of a change in antibacterial regimen may be required.
Failure of treatment due to persisting or relapsing S. aureus bacteremia/endocarditis may be due to reduced daptomycin susceptibility (as evidenced by increasing MIC of the S. aureus isolate) [see Clinical Studies (14.2)].

5.10 Decreased Efficacy in Patients with Moderate Baseline Renal Impairment

Limited data are available from the two Phase 3 complicated skin and skin structure infection (cSSSI) trials regarding clinical efficacy of daptomycin for injection treatment in adult patients with creatinine clearance (CLCR) <50 mL/min; only 31/534 (6%) patients treated with daptomycin for injection in the intent-to-treat (ITT) population had a baseline CLCR <50 mL/min. Table 5 shows the number of adult patients by renal function and treatment group who were clinical successes in the Phase 3 cSSSI trials.

Table 5: Clinical Success Rates by Renal Function and Treatment Group in Phase 3 cSSSI Trials in Adult Patients (Population: ITT)

CLCR | Success Rate n/N (%)
CLCR | Daptomycin for Injection 4 mg/kg every 24h | Comparator
50-70 mL/min | 25/38 (66%) | 30/48 (63%)
30-<50 mL/min | 7/15 (47%) | 20/35 (57%)

In a subgroup analysis of the ITT population in the Phase 3 S. aureus bacteremia/endocarditis trial, clinical success rates, as determined by a treatment-blinded Adjudication Committee [see Clinical Studies (14.2)], in the daptomycin-treated adult patients were lower in patients with baseline CLCR <50 mL/min (see Table 6). A decrease of the magnitude shown in Table 6 was not observed in comparator-treated patients.

Table 6: Adjudication Committee Clinical Success Rates at Test of Cure by Baseline Creatinine Clearance and Treatment Subgroup in the S. aureus Bacteremia/Endocarditis Trial in Adult Patients (Population: ITT)

Baseline CLCR | Success Rate n/N (%)
Baseline CLCR | Daptomycin for Injection 6 mg/kg every 24h |  | Comparator
Baseline CLCR | Bacteremia | Right-Sided Infective Endocarditis | Bacteremia | Right-Sided Infective Endocarditis
>80 mL/min | 30/50 (60%) | 7/14 (50%) | 19/42 (45%) | 5/11 (46%)
50–80 mL/min | 12/26 (46%) | 1/4 (25%) | 13/31 (42%) | 1/2 (50%)
30–<50 mL/min | 2/14 (14%) | 0/1 (0%) | 7/17 (41%) | 1/1 (100%)

Consider these data when selecting antibacterial therapy for use in adult patients with baseline moderate to severe renal impairment.

5.11 Increased International Normalized Ratio (INR)/Prolonged Prothrombin Time

Clinically relevant plasma concentrations of daptomycin have been observed to cause a significant concentration-dependent false prolongation of prothrombin time (PT) and elevation of International Normalized Ratio (INR) when certain recombinant thromboplastin reagents are utilized for the assay [see Drug Interactions (7.2)].

5.12 Development of Drug-Resistant Bacteria

Prescribing Daptomycin for Injection in the absence of a proven or strongly suspected bacterial infection or a prophylactic indication is unlikely to provide benefit to the patient and increases the risk of the development of drug-resistant bacteria.

6 ADVERSE REACTIONS

The following adverse reactions are described, or described in greater detail, in other sections:
• Anaphylaxis/Hypersensitivity Reactions [see Warnings and Precautions (5.1)]
• Myopathy and Rhabdomyolysis [see Warnings and Precautions (5.2)]
• Eosinophilic Pneumonia [see Warnings and Precautions (5.3)]
• Drug Reaction with Eosinophilia and Systemic Symptoms [see Warnings and Precautions (5.4)]
• Tubulointerstitial Nephritis [see Warnings and Precautions (5.5)]
• Peripheral Neuropathy [see Warnings and Precautions (5.6)]
• Increased International Normalized Ratio (INR)/Prolonged Prothrombin Time [see Warnings and Precautions (5.11) and Drug Interactions (7.2)]

6.1 Clinical Trials Experience

Because clinical trials are conducted under widely varying conditions, adverse reaction rates observed in the clinical trials of a drug cannot be directly compared to rates in the clinical trials of another drug and may not reflect the rates observed in clinical practice.

Clinical Trial Experience in Adult Patients
Clinical trials enrolled 1,864 adult patients treated with daptomycin for injection and 1,416 treated with comparator.

Complicated Skin and Skin Structure Infection Trials in Adults
In Phase 3 complicated skin and skin structure infection (cSSSI) trials in adult patients, daptomycin for injection was discontinued in 15/534 (2.8%) patients due to an adverse reaction, while comparator was discontinued in 17/558 (3.0%) patients.
The rates of the most common adverse reactions, organized by body system, observed in adult patients with cSSSI (receiving 4 mg/kg daptomycin for injection) are displayed in Table 7.

Table 7: Incidence of Adverse Reactions that Occurred in ≥2% of Adult Patients in the Daptomycin for Injection Treatment Group and ≥ the Comparator Treatment Group in Phase 3 cSSSI Trials

Adverse Reaction | Adult Patients (%)
Adverse Reaction | Daptomycin for Injection 4 mg/kg (N=534) | Comparator* (N=558)
Gastrointestinal disorders
Diarrhea | 5.2 | 4.3
Nervous system disorders
Headache | 5.4 | 5.4
Dizziness | 2.2 | 2.0
Skin/subcutaneous disorders
Rash | 4.3 | 3.8
Diagnostic investigations
Abnormal liver function tests | 3.0 | 1.6
Elevated CPK | 2.8 | 1.8
Infections
Urinary tract infections | 2.4 | 0.5
Vascular disorders
Hypotension | 2.4 | 1.4
Respiratory disorders
Dyspnea | 2.1 | 1.6

* Comparator: vancomycin (1 g IV q12h) or an anti-staphylococcal semi-synthetic penicillin (i.e., nafcillin, oxacillin, cloxacillin, or flucloxacillin; 4 to 12 g/day IV in divided doses).

Drug-related adverse reactions (possibly or probably drug-related) that occurred in <1% of adult patients receiving daptomycin for injection in the cSSSI trials are as follows:

Body as a Whole: fatigue, weakness, rigors, flushing, hypersensitivity
Blood/Lymphatic System: leukocytosis, thrombocytopenia, thrombocytosis, eosinophilia, increased International Normalized Ratio (INR)
Cardiovascular System: supraventricular arrhythmia
Dermatologic System: eczema
Digestive System: abdominal distension, stomatitis, jaundice, increased serum lactate dehydrogenase
Metabolic/Nutritional System: hypomagnesemia, increased serum bicarbonate, electrolyte disturbance
Musculoskeletal System: myalgia, muscle cramps, muscle weakness, arthralgia
Nervous System: vertigo, mental status change, paresthesia
Special Senses: taste disturbance, eye irritation

S. aureus Bacteremia/Endocarditis Trial in Adults
In the S. aureus bacteremia/endocarditis trial involving adult patients, daptomycin for injection was discontinued in 20/120 (16.7%) patients due to an adverse reaction, while comparator was discontinued in 21/116 (18.1%) patients.

Serious Gram-negative infections (including bloodstream infections) were reported in 10/120 (8.3%) daptomycin-treated patients and 0/115 comparator-treated patients. Comparator-treated patients received dual therapy that included initial gentamicin for 4 days. Infections were reported during treatment and during early and late follow-up. Gram-negative infections included cholangitis, alcoholic pancreatitis, sternal osteomyelitis/mediastinitis, bowel infarction, recurrent Crohn's disease, recurrent line sepsis, and recurrent urosepsis caused by a number of different Gram-negative bacteria.

The rates of the most common adverse reactions, organized by System Organ Class (SOC), observed in adult patients with S. aureus bacteremia/endocarditis (receiving 6 mg/kg daptomycin for injection) are displayed in Table 8.

Table 8: Incidence of Adverse Reactions that Occurred in ≥5% of Adult Patients in the Daptomycin for Injection Treatment Group and ≥ the Comparator Treatment Group in the S. aureus Bacteremia/Endocarditis Trial

Adverse Reaction* | Adult Patients n (%)
Adverse Reaction* | Daptomycin for Injection 6 mg/kg (N=120) | Comparator† (N=116)
Infections and infestations
Sepsis NOS | 6 (5%) | 3 (3%)
Bacteremia | 6 (5%) | 0 (0%)
Gastrointestinal disorders
Abdominal pain NOS | 7 (6%) | 4 (3%)
General disorders and administration site conditions
Chest pain | 8 (7%) | 7 (6%)
Edema NOS | 8 (7%) | 5 (4%)
Respiratory, thoracic and mediastinal disorders
Pharyngolaryngeal pain | 10 (8%) | 2 (2%)
Skin and subcutaneous tissue disorders
Pruritus | 7 (6%) | 6 (5%)
Sweating increased | 6 (5%) | 0 (0%)
Psychiatric disorders
Insomnia | 11 (9%) | 8 (7%)
Investigations
Blood creatine phosphokinase increased | 8 (7%) | 1 (1%)
Vascular disorders
Hypertension NOS | 7 (6%) | 3 (3%)

* NOS, not otherwise specified.

† Comparator: vancomycin (1 g IV q12h) or an anti-staphylococcal semi-synthetic penicillin (i.e., nafcillin, oxacillin, cloxacillin, or flucloxacillin; 2 g IV q4h), each with initial low-dose gentamicin.

The following reactions, not included above, were reported as possibly or probably drug-related in the daptomycin-treated group:

Blood and Lymphatic System Disorders: eosinophilia, lymphadenopathy, thrombocythemia, thrombocytopenia
Cardiac Disorders: atrial fibrillation, atrial flutter, cardiac arrest
Ear and Labyrinth Disorders: tinnitus
Eye Disorders: vision blurred
Gastrointestinal Disorders: dry mouth, epigastric discomfort, gingival pain, hypoesthesia oral
Infections and Infestations: candidal infection NOS, vaginal candidiasis, fungemia, oral candidiasis, urinary tract infection fungal
Investigations: blood phosphorous increased, blood alkaline phosphatase increased, INR increased, liver function test abnormal, alanine aminotransferase increased, aspartate aminotransferase increased, prothrombin time prolonged
Metabolism and Nutrition Disorders: appetite decreased NOS
Musculoskeletal and Connective Tissue Disorders: myalgia
Nervous System Disorders: dyskinesia, paresthesia
Psychiatric Disorders: hallucination NOS
Renal and Urinary Disorders: proteinuria, renal impairment NOS
Skin and Subcutaneous Tissue Disorders: pruritus generalized, rash vesicular

Other Trials in Adults
In Phase 3 trials of community-acquired pneumonia (CAP) in adult patients, the death rate and rates of serious cardiorespiratory adverse events were higher in daptomycin-treated patients than in comparator-treated patients. These differences were due to lack of therapeutic effectiveness of daptomycin in the treatment of CAP in patients experiencing these adverse events [see Indications and Usage (1.4)].

Laboratory Changes in Adults
Complicated Skin and Skin Structure Infection Trials in Adults
In Phase 3 cSSSI trials of adult patients receiving daptomycin at a dose of 4 mg/kg, elevations in CPK were reported as clinical adverse events in 15/534 (2.8%) daptomycin-treated patients, compared with 10/558 (1.8%) comparator-treated patients. Of the 534 patients treated with daptomycin, 1 (0.2%) had symptoms of muscle pain or weakness associated with CPK elevations to greater than 4 times the upper limit of normal (ULN). The symptoms resolved within 3 days and CPK returned to normal within 7 to 10 days after treatment was discontinued [see Warnings and Precautions (5.2)]. Table 9 summarizes the CPK shifts from Baseline through End of Therapy in the cSSSI adult trials.

Table 9: Incidence of CPK Elevations from Baseline during Therapy in Either the Daptomycin for Injection Treatment Group or the Comparator Treatment Group in Phase 3 cSSSI Adult Trials

Change in CPK | All Adult Patients |  |  |  | Adult Patients with Normal CPK at Baseline
Change in CPK | Daptomycin for Injection 4 mg/kg (N=430) |  | Comparator* (N=459) |  | Daptomycin for Injection 4 mg/kg (N=374) |  | Comparator* (N=392)
Change in CPK | % | n | % | n | % | n | % | n
No Increase | 90.7 | 390 | 91.1 | 418 | 91.2 | 341 | 91.1 | 357
Maximum Value >1× ULN† | 9.3 | 40 | 8.9 | 41 | 8.8 | 33 | 8.9 | 35
>2× ULN | 4.9 | 21 | 4.8 | 22 | 3.7 | 14 | 3.1 | 12
>4× ULN | 1.4 | 6 | 1.5 | 7 | 1.1 | 4 | 1.0 | 4
>5× ULN | 1.4 | 6 | 0.4 | 2 | 1.1 | 4 | 0.0 | 0
>10× ULN | 0.5 | 2 | 0.2 | 1 | 0.2 | 1 | 0.0 | 0

Note: Elevations in CPK observed in adult patients treated with daptomycin or comparator were not clinically or statistically significantly different.

* Comparator: vancomycin (1 g IV q12h) or an anti-staphylococcal semi-synthetic penicillin (i.e., nafcillin, oxacillin, cloxacillin, or flucloxacillin; 4 to 12 g/day IV in divided doses).
† ULN (Upper Limit of Normal) is defined as 200 U/L.

S. aureus Bacteremia/Endocarditis Trial in Adults
In the S. aureus bacteremia/endocarditis trial in adult patients, at a dose of 6 mg/kg, 11/120 (9.2%) daptomycin-treated patients, including two patients with baseline CPK levels >500 U/L, had CPK elevations to levels >500 U/L, compared with 1/116 (0.9%) comparator-treated patients. Of the 11 daptomycin-treated patients, 4 had prior or concomitant treatment with an HMG-CoA reductase inhibitor. Three of these 11 daptomycin-treated patients discontinued therapy due to CPK elevation, while the one comparator-treated patient did not discontinue therapy [see Warnings and Precautions (5.2)].

Clinical Trial Experience in Pediatric Patients
Complicated Skin and Skin Structure Infection Trial in Pediatric Patients
The safety of daptomycin for injection was evaluated in one clinical trial (in cSSSI), which included 256 pediatric patients (1 to 17 years of age) treated with intravenous daptomycin for injection and 133 patients treated with comparator agents. Patients were given age-dependent doses once daily for a treatment period of up to 14 days (median treatment period was 3 days). The doses given by age group were as follows: 10mg/kg for 1 to < 2 years, 9 mg/kg for 2 to 6 years, 7mg/kg for 7 to 11 years and 5 mg/kg for 12 to 17 years of age [see Clinical Studies (14)]. Patients treated with daptomycin for injection were (51%) male, (49%) female and (46%) Caucasian and (32%) Asian.

Adverse Reactions Leading to Discontinuation
In the cSSSI study, daptomycin for injection was discontinued in 7/256 (2.7%) patients due to an adverse reaction, while comparator was discontinued in 7/133 (5.3%) patients.

Most Common Adverse Reactions
The rates of the most common adverse reactions, organized by body system, observed in these pediatric patients with cSSSI are displayed in Table 10.

Table 10: Adverse Reactions that Occurred in ≥2% of Pediatric Patients in the Daptomycin for Injection Treatment-Arm and Greater Than or Equal to the Comparator Treatment-Arm in the cSSSI Pediatric Trial

Adverse Reaction | Daptomycin for Injection (N = 256) | Comparator* (N = 133)
Adverse Reaction | n (%) | n (%)
Gastrointestinal disorders
Diarrhea | 18 (7.0) | 7 (5.3)
Vomiting | 7 (2.7) | 1 (0.8)
Abdominal Pain | 5 (2.0) | 0
Skin and subcutaneous tissue disorders
Pruritus | 8 (3.1) | 2 (1.5)
General disorders and administration site conditions
Pyrexia | 10 (3.9) | 4 (3.0)
Investigations
Blood CPK increased | 14 (5.5) | 7 (5.3)
Nervous system disorders
Headache | 7 (2.7) | 3 (2.3)

*Comparators included intravenous therapy with either vancomycin, clindamycin, or an anti-staphylococcal semi-synthetic penicillin (nafcillin, oxacillin or cloxacillin)

The safety profile in the clinical trial of cSSSI pediatric patients was similar to that observed in the cSSSI adult patients.

S. aureus Bacteremia Trial in Pediatric Patients
The safety of daptomycin for injection was evaluated in one clinical trial (in S. aureus bacteremia), which treated 55 pediatric patients with intravenous daptomycin and 26 patients with comparator agents. Patients were given age-dependent doses once daily for a treatment period of up to 42 days (mean duration of IV treatment was 12 days). The doses by age group were as follows: 12 mg/kg for 1 to <6 years, 9 mg/kg for 7 to 11 years and 7 mg/kg for 12 to 17 years of age [see Clinical Studies (14)]. Patients treated with daptomycin were (69%) male and (31%) female. No patients 1 to <2 years of age were enrolled.

Adverse Reactions Leading to Discontinuation
In the bacteremia study, daptomycin for injection was discontinued in 3/55 (5.5%) patients due to an adverse reaction, while comparator was discontinued in 2/26 (7.7%) patients.

Most Common Adverse Reactions
The rates of the most common adverse reactions, organized by body system, observed in these pediatric patients with bacteremia are displayed in Table 11.

Table 11: Incidence of Adverse Reactions that Occurred in ≥5% of Pediatric Patients in the Daptomycin for Injection Treatment- Arm and Greater Than or Equal to the Comparator Treatment-Arm in the Pediatric Bacteremia Trial

Adverse Reaction | Daptomycin for Injection (N = 55) | Comparator* (N = 26)
Adverse Reaction | n (%) | n (%)
Gastrointestinal disorders
Vomiting | 6 (10.9) | 2 (7.7)
Investigations
Blood CPK increased | 4 (7.3) | 0

*Comparators included intravenous therapy with either vancomycin, cefazolin, or an anti-staphylococcal semi-synthetic penicillin (nafcillin, oxacillin or cloxacillin)

6.2 Postmarketing Experience

The following adverse reactions have been identified during post-approval use of daptomycin for injection. Because these reactions are reported voluntarily from a population of uncertain size, it is not always possible to reliably estimate their frequency or establish a causal relationship to drug exposure.

Blood and lymphatic system disorders: anemia, thrombocytopenia

General and administration site conditions: pyrexia

Immune System Disorders: anaphylaxis; hypersensitivity reactions, including angioedema, pruritus, hives, shortness of breath, difficulty swallowing, truncal erythema, and pulmonary eosinophilia [see Contraindications (4) and Warnings and Precautions (5.1)]

Infections and Infestations: Clostridioides difficile–associated diarrhea [see Warnings and Precautions (5.8)]

Laboratory Investigations: platelet count decreased; hyperkalemia

Musculoskeletal Disorders: myoglobin increased; rhabdomyolysis (some reports involved patients treated concurrently with daptomycin and HMG-CoA reductase inhibitors) [see Warnings and Precautions (5.2), Drug Interactions (7.1), and Clinical Pharmacology (12.3)]

Respiratory, Thoracic, and Mediastinal Disorders: cough, eosinophilic pneumonia, organizing pneumonia [see Warnings and Precautions (5.3)]
Nervous System Disorders: peripheral neuropathy [see Warnings and Precautions (5.6)]

Skin and Subcutaneous Tissue Disorders: serious skin reactions, including drug reaction with eosinophilia and systemic symptoms (DRESS), vesiculobullous rash (with or without mucous membrane involvement, including Stevens-Johnson syndrome [SJS] and toxic epidermal necrolysis [TEN]), and acute generalized exanthematous pustulosis [see Warnings and Precautions (5.4)]

Gastrointestinal Disorders: nausea, vomiting

Renal and urinary disorders: acute kidney injury, renal insufficiency, renal failure, and tubulointerstitial nephritis (TIN) [see Warnings and Precautions (5.5)]

Special Senses: visual disturbances

7 DRUG INTERACTIONS

7.1 HMG-CoA Reductase Inhibitors

In healthy adult subjects, concomitant administration of daptomycin for injection and simvastatin had no effect on plasma trough concentrations of simvastatin, and there were no reports of skeletal myopathy [see Clinical Pharmacology (12.3)].

However, inhibitors of HMG-CoA reductase may cause myopathy, which is manifested as muscle pain or weakness associated with elevated levels of creatine phosphokinase (CPK). In the adult Phase 3 S. aureus bacteremia/endocarditis trial, some patients who received prior or concomitant treatment with an HMG-CoA reductase inhibitor developed elevated CPK [see Adverse Reactions (6.1)]. Experience with the coadministration of HMG-CoA reductase inhibitors and daptomycin in patients is limited; therefore, consideration should be given to suspending use of HMG-CoA reductase inhibitors temporarily in patients receiving Daptomycin for Injection.

7.2 Drug-Laboratory Test Interactions

Clinically relevant plasma concentrations of daptomycin have been observed to cause a significant concentration-dependent false prolongation of prothrombin time (PT) and elevation of International Normalized Ratio (INR) when certain recombinant thromboplastin reagents are utilized for the assay. The possibility of an erroneously elevated PT/INR result due to interaction with a recombinant thromboplastin reagent may be minimized by drawing specimens for PT or INR testing near the time of trough plasma concentrations of daptomycin. However, sufficient daptomycin concentrations may be present at trough to cause interaction.

If confronted with an abnormally high PT/INR result in a patient being treated with Daptomycin for Injection, it is recommended that clinicians:
1. Repeat the assessment of PT/INR, requesting that the specimen be drawn just prior to the next daptomycin dose (i.e., at trough concentration). If the PT/INR value obtained at trough remains substantially elevated above what would otherwise be expected, consider evaluating PT/INR utilizing an alternative method.
2. Evaluate for other causes of abnormally elevated PT/INR results.

8 USE IN SPECIFIC POPULATIONS

8.1 Pregnancy

Risk Summary

Limited published data on use of daptomycin for injection in pregnant women are insufficient to inform a drug-associated risk for major birth defects and miscarriage. In animal reproduction studies performed in rats and rabbits daptomycin was administered intravenously during organogenesis at doses 2 and 4-times, respectively, the recommended 6 mg/kg human dose (on a body surface area basis). No evidence of adverse developmental outcomes was observed.

The background risk of major birth defects and miscarriage for the indicated population is unknown. All pregnancies have a background risk of birth defect, loss, or other adverse outcomes. In the U.S. general population, the estimated background risk of major birth defects and miscarriage in clinically recognized pregnancies is 2 to 4% and 15 to 20%, respectively.

Data
Animal Data
In pregnant rats, daptomycin was administered intravenously at doses of 5, 20, or 75 mg/kg/day during the gestation days 6 to 18. Maternal body weight gain was decreased at 75 mg/kg/day. No embryo/fetal effects were noted at the highest dose of 75 mg/kg/day, a dose approximately 2-fold higher than in humans at the recommended maximum dose of 6mg/kg (based on body surface area).
In pregnant rabbits, daptomycin was administered intravenously at doses of 5, 20, or 75 mg/kg/day during the gestation days 6 to 15. Maternal body weight gain and food consumption were decreased at 75 mg/kg/day. No embryo/fetal effects were noted at the highest dose of 75 mg/kg/day, a dose approximately 4-fold higher than in humans at the maximum recommended dose of 6mg/kg (based on body surface area).
In a combined fertility and pre/postnatal development study, daptomycin was administered intravenously to female rats at doses of 2, 25, 75 mg/kg/day from 14-days pre-mating through lactation/postpartum day 20). No effects on pre/postnatal development were observed up to the highest dose of 75 mg/kg/day, a dose approximately 2-fold higher than the maximum recommended human dose of 6 mg/kg (based on body surface area)^1.

8.2 Lactation

Risk Summary
Limited published data report that daptomycin is present in human milk at infant doses of 0.1% of the maternal dose (see Data)^2,3,4. There is no information on the effects of daptomycin on the breastfed infant or the effects of daptomycin on milk production. The developmental and health benefits of breastfeeding should be considered along with the mother's clinical need for Daptomycin for Injection and any potential adverse effects on the breastfed infant from Daptomycin for Injection or from the underlying maternal condition.

8.4 Pediatric Use

The safety and effectiveness of daptomycin for injection in the treatment of cSSSI and S. aureus bloodstream infections (bacteremia) have been established in the age groups 1 to 17 years of age. Use of daptomycin for injection in these age groups is supported by evidence from adequate and well-controlled studies in adults, with additional data from pharmacokinetic studies in pediatric patients, and from safety, efficacy and PK studies in pediatric patients with cSSSI and S. aureus bloodstream infections [see Adverse Reactions (6.1), Clinical Pharmacology (12.3), and Clinical Studies (14.1, 14.2)].

Safety and effectiveness in pediatric patients below the age of one year have not been established. Avoid use of Daptomycin for Injection in pediatric patients younger than one year of age due to the risk of potential effects on muscular, neuromuscular, and/or nervous systems (either peripheral and/or central) observed in neonatal dogs [see Warnings and Precautions (5.7) and Nonclinical Toxicology (13.2)].

Daptomycin for Injection is not indicated in pediatric patients with renal impairment because dosage has not been established in these patients.

Daptomycin for Injection has not been studied in pediatric patients with other bacterial infections.

8.5 Geriatric Use

Of the 534 adult patients treated with daptomycin for injection in Phase 3 controlled clinical trials of complicated skin and skin structure infections (cSSSI), 27% were 65 years of age or older and 12% were 75 years of age or older. Of the 120 adult patients treated with daptomycin in the Phase 3 controlled clinical trial of S. aureus bacteremia/endocarditis, 25% were 65 years of age or older and 16% were 75 years of age or older. In Phase 3 adult clinical trials of cSSSI and S. aureus bacteremia/endocarditis, clinical success rates were lower in patients ≥65 years of age than in patients <65 years of age. In addition, treatment-emergent adverse events were more common in patients ≥65 years of age than in patients <65 years of age.

The exposure of daptomycin was higher in healthy elderly subjects than in healthy young adult subjects. However, no adjustment of Daptomycin for Injection dosage is warranted for elderly patients with creatinine clearance (CLCR) ≥30 mL/min [see Dosage and Administration (2.6) and Clinical Pharmacology (12.3)].

8.6 Patients with Renal Impairment

Daptomycin is eliminated primarily by the kidneys; therefore, a modification of daptomycin dosage interval is recommended for adult patients with CLCR <30 mL/min, including patients receiving hemodialysis or continuous ambulatory peritoneal dialysis (CAPD). In adult patients with renal impairment, both renal function and creatine phosphokinase (CPK) should be monitored more frequently than once weekly [see Dosage and Administration (2.6), Warnings and Precautions (5.2, 5.10), and Clinical Pharmacology (12.3)].

The dosage regimen for Daptomycin for Injection in pediatric patients with renal impairment has not been established.

10 OVERDOSAGE

In the event of overdosage, supportive care is advised with maintenance of glomerular filtration. Daptomycin is cleared slowly from the body by hemodialysis (approximately 15% of the administered dose is removed over 4 hours) and by peritoneal dialysis (approximately 11% of the administered dose is removed over 48 hours). The use of high-flux dialysis membranes during 4 hours of hemodialysis may increase the percentage of dose removed compared with that removed by low-flux membranes.

11 DESCRIPTION

Daptomycin for Injection contains daptomycin, a cyclic lipopeptide antibacterial agent derived from the fermentation of Streptomyces roseosporus. The chemical name is N-decanoyl-L-tryptophyl-D-asparaginyl-L-aspartyl-L-threonylglycyl-L-ornithyl-L- aspartyl-D-alanyl-L-aspartylglycyl-D-seryl-threo-3-methyl-L-glutamyl-3-anthraniloyl-L- alanine ε1-lactone. The empirical formula is C72H101N17O26; the molecular weight is 1620.67. The chemical structure is:

Daptomycin for Injection is supplied in a single-dose vial as a sterile, preservative-free, pale yellow to light brown lyophilized powder containing 350 mg or 500 mg of daptomycin for intravenous (IV) use following reconstitution with Sterile Water for Injection [see Dosage and Administration (2.7)]. Freshly reconstituted solutions of Daptomycin for Injection range in color from pale yellow to light brown.

- Daptomycin for Injection 350 mg per vial, contains 350 mg daptomycin and 210 mg arginine hydrochloride. Hydrochloric acid and/or sodium hydroxide is used to adjust the pH.
- Daptomycin for Injection 500 mg per vial contains 500 mg daptomycin, and 300 mg arginine hydrochloride. Hydrochloric acid and/or sodium hydroxide is used to adjust the pH.

12 CLINICAL PHARMACOLOGY

12.1 Mechanism of Action

Daptomycin is an antibacterial drug [see Clinical Pharmacology (12.4)].

12.2 Pharmacodynamics

Based on animal models of infection, the antimicrobial activity of daptomycin for injection appears to correlate with the AUC/MIC (area under the concentration-time curve/minimum inhibitory concentration) ratio for certain pathogens, including S. aureus. The principal pharmacokinetic/pharmacodynamic parameter best associated with clinical and microbiological cure has not been elucidated in clinical trials with daptomycin for injection.

12.3 Pharmacokinetics

Daptomycin Administered over a 30-Minute Period in Adults
The mean and standard deviation (SD) pharmacokinetic parameters of daptomycin at steady-state following intravenous (IV) administration of daptomycin for injection over a 30-minute period at 4 to 12 mg/kg every 24h to healthy young adults are summarized in Table 12.

Table 12: Mean (SD) Daptomycin Pharmacokinetic Parameters in Healthy Adult Volunteers at Steady-State

Dose*† (mg/kg) | Pharmacokinetic Parameters‡
Dose*† (mg/kg) | AUC0-24 (mcg∙h/mL) | t1/2 (h) | VSS (L/kg) | CLT (mL/h/kg) | Cmax (mcg/mL)
4 (N=6) | 494 (75) | 8.1 (1.0) | 0.096 (0.009) | 8.3 (1.3) | 57.8 (3.0)
6 (N=6) | 632 (78) | 7.9 (1.0) | 0.101 (0.007) | 9.1 (1.5) | 93.9 (6.0)
8 (N=6) | 858 (213) | 8.3 (2.2) | 0.101 (0.013) | 9.0 (3.0) | 123.3 (16.0)
10 (N=9) | 1039 (178) | 7.9 (0.6) | 0.098 (0.017) | 8.8 (2.2) | 141.1 (24.0)
12 (N=9) | 1277 (253) | 7.7 (1.1) | 0.097 (0.018) | 9.0 (2.8) | 183.7 (25.0)

* Daptomycin for injection was administered by IV infusion over a 30-minute period.
† Doses of daptomycin for injection in excess of 6 mg/kg have not been approved.
‡ AUC0-24, area under the concentration-time curve from 0 to 24 hours; t1/2, elimination half-life;

VSS, volume of distribution at steady-state; CLT, total plasma clearance; Cmax, maximum plasma concentration.

Daptomycin pharmacokinetics were generally linear and time-independent at daptomycin doses of 4 to 12 mg/kg every 24h administered by IV infusion over a 30-minute period for up to 14 days. Steady-state trough concentrations were achieved by the third daily dose. The mean (SD) steady-state trough concentrations attained following the administration of 4, 6, 8, 10, and 12 mg/kg every 24h were 5.9 (1.6), 6.7 (1.6), 10.3 (5.5), 12.9 (2.9), and 13.7 (5.2) mcg/mL, respectively.

Daptomycin for Injection Administered over a 2-Minute Period in Adults

Following IV administration of daptomycin for injection over a 2-minute period to healthy adult volunteers at doses of 4 mg/kg (N=8) and 6 mg/kg (N=12), the mean (SD) steady-state systemic exposure (AUC) values were 475 (71) and 701 (82) mcg∙h/mL, respectively. Values for maximum plasma concentration (Cmax) at the end of the 2-minute period could not be determined adequately in this study. However, using pharmacokinetic parameters from 14 healthy adult volunteers who received a single dose of daptomycin 6 mg/kg IV administered over a 30-minute period in a separate study, steady-state Cmax values were simulated for daptomycin 4 and 6 mg/kg IV administered over a 2-minute period. The simulated mean (SD) steady-state Cmax values were 77.7 (8.1) and 116.6 (12.2) mcg/mL, respectively.

Distribution
Daptomycin is reversibly bound to human plasma proteins, primarily to serum albumin, in a concentration-independent manner. The overall mean binding ranges from 90 to 93%.
In clinical studies, mean serum protein binding in adult subjects with creatinine clearance (CLCR) ≥30 mL/min was comparable to that observed in healthy adult subjects with normal renal function. However, there was a trend toward decreasing serum protein binding among subjects with CLCR <30 mL/min (88%), including those receiving hemodialysis (86%) and continuous ambulatory peritoneal dialysis (CAPD) (84%). The protein binding of daptomycin in adult subjects with moderate hepatic impairment (Child-Pugh Class B) was similar to that in healthy adult subjects.

The volume of distribution at steady-state (VSS) of daptomycin in healthy adult subjects was approximately 0.1 L/kg and was independent of dose.

Metabolism
In in vitro studies, daptomycin was not metabolized by human liver microsomes.
In 5 healthy adults after infusion of radiolabeled ^14C-daptomycin, the plasma total radioactivity was similar to the concentration determined by microbiological assay. Inactive metabolites were detected in urine, as determined by the difference between total radioactive concentrations and microbiologically active concentrations. In a separate study, no metabolites were observed in plasma on Day 1 following the administration of daptomycin at 6 mg/kg to adult subjects. Minor amounts of three oxidative metabolites and one unidentified compound were detected in urine. The site of metabolism has not been identified.

Excretion
Daptomycin is excreted primarily by the kidneys. In a mass balance study of 5 healthy adult subjects using radiolabeled daptomycin, approximately 78% of the administered dose was recovered from urine based on total radioactivity (approximately 52% of the dose based on microbiologically active concentrations), and 5.7% of the administered dose was recovered from feces (collected for up to 9 days) based on total radioactivity.

Specific Populations

Patients with Renal Impairment
Population-derived pharmacokinetic parameters were determined for infected adult patients (complicated skin and skin structure infections [cSSSI] and S. aureus bacteremia) and noninfected adult subjects with various degrees of renal function (Table 13). Total plasma clearance (CLT), elimination half-life (t1/2), and volume of distribution at steady-state (VSS) in patients with cSSSI were similar to those in patients with S. aureus bacteremia. Following administration of daptomycin for injection 4 mg/kg every 24h by IV infusion over a 30-minute period, the mean CLT was 9%, 22%, and 46% lower among subjects and patients with mild (CLCR 50–80 mL/min), moderate (CLCR 30–<50 mL/min), and severe (CLCR <30 mL/min) renal impairment, respectively, than in those with normal renal function (CLCR >80 mL/min). The mean steady-state systemic exposure (AUC), t1/2, and VSS increased with decreasing renal function, although the mean AUC for patients with CLCR 30–80 mL/min was not markedly different from the mean AUC for patients with normal renal function. The mean AUC for patients with CLCR <30 mL/min and for patients on dialysis (CAPD and hemodialysis dosed post-dialysis) was approximately 2 and 3 times higher, respectively, than for patients with normal renal function. The mean Cmax ranged from 60 to 70 mcg/mL in patients with CLCR ≥30 mL/min, while the mean Cmax for patients with CLCR <30 mL/min ranged from 41 to 58 mcg/mL. After administration of daptomycin for injection 6 mg/kg every 24h by IV infusion over a 30-minute period, the mean Cmax ranged from 80 to 114 mcg/mL in patients with mild to moderate renal impairment and was similar to that of patients with normal renal function.

Table 13: Mean (SD) Daptomycin Population Pharmacokinetic Parameters Following Infusion of Daptomycin for Injection 4 mg/kg or 6 mg/kg to Infected Adult Patients and Noninfected Adult Subjects with Various Degrees of Renal Function

Renal Function | Pharmacokinetic Parameters*
Renal Function | t1/2 (h) 4 mg/kg | Vss† (L/kg) 4 mg/kg | CLT† (mL/h/kg) 4 mg/kg | AUC0-∞† (mcg∙h/mL) 4 mg/kg | AUCss‡ (mcg∙h/mL) 6 mg/kg | Cmin,ss‡ (mcg/mL) 6 mg/kg
Normal (CLCR >80 mL/min) | 9.39 (4.74) N=165 | 0.13 (0.05) N=165 | 10.9 (4.0) N=165 | 417 (155) N=165 | 545 (296) N=62 | 6.9 (3.5) N=61
Mild Renal Impairment (CLCR 50–80 mL/min) | 10.75 (8.36) N=64 | 0.12 (0.05) N=64 | 9.9 (4.0) N=64 | 466 (177) N=64 | 637 (215) N=29 | 12.4 (5.6) N=29
Moderate Renal Impairment (CLCR 30– <50 mL/min) | 14.70 (10.50) N=24 | 0.15 (0.06) N=24 | 8.5 (3.4) N=24 | 560 (258) N=24 | 868 (349) N=15 | 19.0 (9.0) N=14
Severe Renal Impairment (CLCR <30 mL/min) | 27.83 (14.85) N=8 | 0.20 (0.15) N=8 | 5.9 (3.9) N=8 | 925 (467) N=8 | 1050 (892) N=2 | 24.4 (21.4) N=2
Hemodialysis | 30.51 (6.51) N=16 | 0.16 (0.04) N=16 | 3.9 (2.1) N=16 | 1193 (399) N=16 | NA | NA
CAPD | 27.56 (4.53) N=5 | 0.11 (0.02) N=5 | 2.9 (0.4) N=5 | 1409 (238) N=5 | NA | NA

Note: daptomycin for injection was administered over a 30-minute period.
* CLCR, creatinine clearance estimated using the Cockcroft-Gault equation with actual body weight; CAPD, continuous ambulatory peritoneal dialysis; AUC0-∞, area under the concentration-time curve extrapolated to infinity; AUCSS, area under the concentration-time curve calculated over the 24-hour dosing interval at steady-state; Cmin,SS, trough concentration at steady-state; NA, not applicable.
† Parameters obtained following a single dose from patients with complicated skin and skin structure infections and healthy subjects.
‡ Parameters obtained at steady-state from patients with S. aureus bacteremia.

Because renal excretion is the primary route of elimination, adjustment of Daptomycin for Injection dosage interval is necessary in adult patients with severe renal impairment (CLCR <30 mL/min) [see Dosage and Administration (2.6)].

Patients with Hepatic Impairment
The pharmacokinetics of daptomycin were evaluated in 10 adult subjects with moderate hepatic impairment (Child-Pugh Class B) and compared with those in healthy adult volunteers (N=9) matched for gender, age, and weight. The pharmacokinetics of daptomycin were not altered in subjects with moderate hepatic impairment. No dosage adjustment is warranted when Daptomycin for Injection is administered to patients with mild to moderate hepatic impairment. The pharmacokinetics of daptomycin in patients with severe hepatic impairment (Child-Pugh Class C) have not been evaluated.

Gender
No clinically significant gender-related differences in daptomycin pharmacokinetics have been observed. No dosage adjustment is warranted based on gender when daptomycin is administered.

Geriatric Patients
The pharmacokinetics of daptomycin were evaluated in 12 healthy elderly subjects (≥75 years of age) and 11 healthy young adult controls (18 to 30 years of age). Following administration of a single 4 mg/kg dose of daptomycin for injection by IV infusion over a 30-minute period, the mean total clearance of daptomycin was approximately 35% lower and the mean AUC0-∞ was approximately 58% higher in elderly subjects than in healthy young adult subjects. There were no differences in Cmax [see Use in Specific Populations (8.5)].

Obese Patients

The pharmacokinetics of daptomycin were evaluated in 6 moderately obese (Body Mass Index [BMI] 25 to 39.9 kg/m^2) and 6 extremely obese (BMI ≥40 kg/m^2) adult subjects and controls matched for age, gender, and renal function. Following administration of daptomycin for injection by IV infusion over a 30-minute period as a single 4 mg/kg dose based on total body weight, the total plasma clearance of daptomycin normalized to total body weight was approximately 15% lower in moderately obese subjects and 23% lower in extremely obese subjects than in nonobese controls. The AUC0-∞ of daptomycin was approximately 30% higher in moderately obese subjects and 31% higher in extremely obese subjects than in nonobese controls. The differences were most likely due to differences in the renal clearance of daptomycin. No adjustment of daptomycin dosage is warranted in obese patients.

Pediatric Patients
The pharmacokinetics of daptomycin in pediatric subjects was evaluated in 3 single-dose pharmacokinetic studies. In general, body weight-normalized total body clearance in pediatric patients was higher than in adults and increased with a decrease of age, whereas elimination half-life tends to decrease with a decrease of age. Body weight- normalized total body clearance and elimination half-life of daptomycin in children 2 to 6 years of age were similar at different doses.

A study was conducted to assess safety, efficacy, and pharmacokinetics of daptomycin in pediatric patients (1 to 17 years old, inclusive) with cSSSI caused by Gram-positive pathogens. Patients were enrolled into 4 age groups [see Clinical Studies (14.1)], and intravenous daptomycin for injection doses of 5 to 10 mg/kg once daily were administered. Following administration of multiple doses, daptomycin exposure (AUCSS and Cmax,SS) was similar across different age groups after dose adjustment based on body weight and age (Table 14).

Table 14: Mean (SD) Daptomycin Population Pharmacokinetic Parameters in cSSSI Pediatric Patients

Age | Pharmacokinetic Parameters
Age | Dose (mg/kg) | Infusion Duration (min) | AUCss (mcg∙h/mL) | t1/2 (h) | Vss (mL) | CLT (mL/h/kg) | Cmax,ss (mcg/mL)
12 to 17 years (N=6) | 5 | 30 | 434 (67.9) | 7.1 (0.9) | 8200 (3250) | 11.8 (2.15) | 76.4 (6.75)
7 to 11 years (N=2) | 7 | 30 | 543* | 6.8* | 4470* | 13.2* | 92.4*
2 to 6 years (N=7) | 9 | 60 | 452 (93.1) | 4.6 (0.8) | 2750 (832) | 20.8 (4.29) | 90.3 (14.0)
1 to less than 2 years (N=27) | 10 | 60 | 462 (138) | 4.8 (0.6) | 1670 (446) | 23.1 (5.43) | 81.6 (20.7)

AUCss, area under the concentration-time curve at steady state; CLT, clearance normalized to body weight; Vss, volume of distribution at steady state; t1/2;, terminal half-life
* Mean is calculated from N=2

A study was conducted to assess safety, efficacy, and pharmacokinetics of daptomycin in pediatric patients with S. aureus bacteremia. Patients were enrolled into 3 age groups [see Clinical Studies (14.2)], and intravenous doses of 7 to 12 mg/kg once daily were administered. Following administration of multiple doses, daptomycin exposure (AUCSS and Cmax,SS) was similar across different age groups after dose adjustment based on body weight and age (Table 15).

Table 15: Mean (SD) of Daptomycin Pharmacokinetics in Bacteremia Pediatric Patients

Age | Pharmacokinetic Parameters
Age | Dose (mg/kg) | Infusion Duration (min) | AUCss (mcg∙h/mL) | t1/2 (h) | Vss (mL) | CLT (mL/h/kg) | Cmax,ss (mcg/mL)
12 to 17 years (N=13) | 7 | 30 | 656 (334) | 7.5 (2.3) | 6420 (1980) | 12.4 (3.9) | 104 (35.5)
7 to 11 years (N=19) | 9 | 30 | 579 (116) | 6.0 (0.8) | 4510 (1470) | 15.9 (2.8) | 104 (14.5)
2 to 6 years (N=19) | 12 | 60 | 620 (109) | 5.1 (0.6) | 2200 (570) | 19.9 (3.4) | 106 (12.8)

AUCSS, area under the concentration-time curve at steady state; CLT, clearance normalized to body weight; VSS, volume of distribution at steady state; t1/2 terminal half-life
No patients 1 to <2 years of age were enrolled in the study. Simulation using a population pharmacokinetic model demonstrated that the AUCSS of daptomycin in pediatric patients 1 to <2 years of age receiving 12 mg/kg once daily would be comparable to that in adult patients receiving 6 mg/kg once daily.

Drug Interaction Studies
In Vitro Studies
In vitro studies with human hepatocytes indicate that daptomycin does not inhibit or induce the activities of the following human cytochrome P450 isoforms: 1A2, 2A6, 2C9, 2C19, 2D6, 2E1, and 3A4. It is unlikely that daptomycin will inhibit or induce the metabolism of drugs metabolized by the P450 system.

Aztreonam
In a study in which 15 healthy adult subjects received a single dose of daptomycin for injection 6 mg/kg IV and a combination dose of Daptomycin for Injection 6 mg/kg IV and aztreonam 1 g IV, administered over a 30-minute period, the Cmax and AUC0-∞ of daptomycin were not significantly altered by aztreonam.

Tobramycin
In a study in which 6 healthy adult males received a single dose of daptomycin for injection 2 mg/kg IV, tobramycin 1 mg/kg IV, and both in combination, administered over a 30-minute period, the mean Cmax and AUC0-∞ of daptomycin were 12.7% and 8.7% higher, respectively, when daptomycin was coadministered with tobramycin. The mean Cmax and AUC0-∞ of tobramycin were 10.7% and 6.6% lower, respectively, when tobramycin was coadministered with daptomycin. These differences were not statistically significant. The interaction between daptomycin and tobramycin with a clinical dose of daptomycin is unknown.

Warfarin
In 16 healthy adult subjects, administration of daptomycin for injection 6 mg/kg every 24h by IV infusion over a 30-minute period for 5 days, with coadministration of a single oral dose of warfarin (25 mg) on the 5th day, had no significant effect on the pharmacokinetics of either drug and did not significantly alter the INR (International Normalized Ratio).

Simvastatin
In 20 healthy adult subjects on a stable daily dose of simvastatin 40 mg, administration of daptomycin for injection 4 mg/kg every 24h by IV infusion over a 30-minute period for 14 days (N=10) had no effect on plasma trough concentrations of simvastatin and was not associated with a higher incidence of adverse events, including skeletal myopathy, than in subjects receiving placebo once daily (N=10) [see Warnings and Precautions (5.2) and Drug Interactions (7.1)].

Probenecid
Concomitant administration of probenecid (500 mg 4 times daily) and a single dose of daptomycin for injection 4 mg/kg by IV infusion over a 30-minute period in adults did not significantly alter the Cmax or AUC0-∞ of daptomycin.

12.4 Microbiology

Daptomycin belongs to the cyclic lipopeptide class of antibacterials. Daptomycin has clinical utility in the treatment of infections caused by aerobic, Gram-positive bacteria. The in vitro spectrum of activity of daptomycin encompasses most clinically relevant Gram-positive pathogenic bacteria.

Daptomycin exhibits rapid, concentration-dependent bactericidal activity against Gram-positive bacteria in vitro. This has been demonstrated both by time-kill curves and by MBC/MIC (minimum bactericidal concentration/minimum inhibitory concentration) ratios using broth dilution methodology. Daptomycin maintained bactericidal activity in vitro against stationary phase S. aureus in simulated endocardial vegetations. The clinical significance of this is not known.

Mechanism of Action
Daptomycin binds to bacterial cell membranes and causes a rapid depolarization of membrane potential. This loss of membrane potential causes inhibition of DNA, RNA, and protein synthesis, which results in bacterial cell death.

Resistance
The mechanism(s) of daptomycin resistance is not fully understood. Currently, there are no known transferable elements that confer resistance to daptomycin.

Interactions with Other Antibacterials
In vitro studies have investigated daptomycin interactions with other antibacterials. Antagonism, as determined by kill curve studies, has not been observed. In vitro synergistic interactions of daptomycin with aminoglycosides, β-lactam antibacterials, and rifampin have been shown against some isolates of staphylococci (including some methicillin-resistant isolates) and enterococci (including some vancomycin-resistant isolates).

Complicated Skin and Skin Structure Infection (cSSSI) Trials in Adults
The emergence of daptomycin non-susceptible isolates occurred in 2 infected patients across the set of Phase 2 and pivotal Phase 3 clinical trials of cSSSI in adult patients. In one case, a non-susceptible S. aureus was isolated from a patient in a Phase 2 trial who received daptomycin at less than the protocol-specified dose for the initial 5 days of therapy. In the second case, a non-susceptible Enterococcus faecalis was isolated from a patient with an infected chronic decubitus ulcer who was enrolled in a salvage trial.

S. aureus Bacteremia/Endocarditis and Other Post-Approval Trials in Adults
In subsequent clinical trials in adult patients, non-susceptible isolates were recovered. S. aureus was isolated from a patient in a compassionate-use trial and from 7 patients in the S. aureus bacteremia/endocarditis trial [see Clinical Studies (14.2)]. An E. faecium was isolated from a patient in a vancomycin-resistant enterococci trial.

Antimicrobial Activity
Daptomycin has been shown to be active against most isolates of the following microorganisms both in vitro and in clinical infections [see Indications and Usage (1)].

Gram-Positive Bacteria

Enterococcus faecalis (vancomycin-susceptible isolates only)
Staphylococcus aureus (including methicillin-resistant isolates)
Streptococcus agalactiae
Streptococcus dysgalactiae subsp. equisimilis
Streptococcus pyogenes

The following in vitro data are available, but their clinical significance is unknown. At least 90 percent of the following bacteria exhibit an in vitro minimum inhibitory concentration (MIC) less than or equal to the susceptible breakpoint for daptomycin against isolates of similar genus or organism group. However, the efficacy of daptomycin in treating clinical infections caused by these bacteria has not been established in adequate and well-controlled clinical trials.

Gram-Positive Bacteria
Corynebacterium jeikeium
Enterococcus faecalis (vancomycin-resistant isolates)
Enterococcus faecium (including vancomycin-resistant isolates)
Staphylococcus epidermidis (including methicillin-resistant isolates)
Staphylococcus haemolyticus

Susceptibility Testing

For specific information regarding susceptibility test interpretive criteria and associated test methods and quality control standards recognized by FDA for daptomycin, please see:

https://www.fda.gov/STIC

13 NONCLINICAL TOXICOLOGY

13.1 Carcinogenesis, Mutagenesis, Impairment of Fertility

Long-term carcinogenicity studies in animals have not been conducted to evaluate the carcinogenic potential of daptomycin for injection. However, neither mutagenic nor clastogenic potential was found in a battery of genotoxicity tests, including the Ames assay, a mammalian cell gene mutation assay, a test for chromosomal aberrations in Chinese hamster ovary cells, an in vivo micronucleus assay, an in vitro DNA repair assay, and an in vivo sister chromatid exchange assay in Chinese hamsters.

Daptomycin did not affect the fertility or reproductive performance of male and female rats when administered intravenously at doses of 25, 75, or 150 mg/kg/day, which is approximately up to 9 times the estimated human exposure level based upon AUCs (or approximately up to 4 times the recommended human dose of 6 mg/kg based on body surface area comparison).

13.2 Animal Toxicology and/or Pharmacology

Adult Animals
In animals, daptomycin administration has been associated with effects on skeletal muscle. However, there were no changes in cardiac or smooth muscle. Skeletal muscle effects were characterized by microscopic degenerative/regenerative changes and variable elevations in creatine phosphokinase (CPK). No fibrosis or rhabdomyolysis was evident in repeat-dose studies up to the highest doses tested in rats (150 mg/kg/day) and dogs (100 mg/kg/day). The degree of skeletal myopathy showed no increase when treatment was extended from 1 month to up to 6 months. Severity was dose-dependent. All muscle effects, including microscopic changes, were fully reversible within 30 days following the cessation of dosing.

In adult animals, effects on peripheral nerve (characterized by axonal degeneration and frequently accompanied by significant losses of pate lar reflex, gag reflex, and pain perception) were observed at daptomycin doses higher than those associated with skeletal myopathy. Deficits in the dogs' pate lar reflexes were seen within 2 weeks after the start of treatment at 40 mg/kg/day (9 times the human Cmax at the 6 mg/kg/day dose), with some clinical improvement noted within 2 weeks after the cessation of dosing. However, at 75 mg/kg/day for 1 month, 7 of 8 dogs failed to regain full pate lar reflex responses within a 3-month recovery period. In a separate study in dogs receiving doses of 75 and 100 mg/kg/day for 2 weeks, minimal residual histological changes were noted at 6 months after the cessation of dosing. However, recovery of peripheral nerve function was evident.

Tissue distribution studies in rats showed that daptomycin is retained in the kidney but appears to penetrate the blood-brain barrier only minimally following single and multiple doses.

Juvenile Animals
Target organs of daptomycin-related effects in 7-week-old juvenile dogs were skeletal muscle and nerve, the same target organs as in adult dogs. In juvenile dogs, nerve effects were noted at lower daptomycin blood concentrations than in adult dogs following 28 days of dosing. In contrast to adult dogs, juvenile dogs also showed evidence of effects in nerves of the spinal cord as well as peripheral nerves after 28 days of dosing. No nerve effects were noted in juvenile dogs following 14 days of dosing at doses up to 75 mg/kg/day.

Administration of daptomycin to 7-week-old juvenile dogs for 28 days at doses of 50 mg/kg/day produced minimal degenerative effects on the peripheral nerve and spinal cord in several animals, with no corresponding clinical signs. A dose of 150 mg/kg/day for 28 days produced minimal degeneration in the peripheral nerve and spinal cord as well as minimal to mild degeneration of the skeletal muscle in a majority of animals, accompanied by slight to severe muscle weakness evident in most dogs. Following a 28-day recovery phase, microscopic examination revealed recovery of the skeletal muscle and the ulnar nerve effects, but nerve degeneration in the sciatic nerve and spinal cord was still observed in all 150 mg/kg/day dogs.

Following once-daily administration of daptomycin to juvenile dogs for 28 days, microscopic effects in nerve tissue were noted at a Cmax value of 417 mcg/mL, which is approximately 3-fold less than the Cmax value associated with nerve effects in adult dogs treated once daily with daptomycin for 28 days (1308 mcg/mL).

Neonatal Animals
Neonatal dogs (4 to 31 days old) were more sensitive to daptomycin-related adverse nervous system and/or muscular system effects than either juvenile or adult dogs. In neonatal dogs, adverse nervous system and/or muscular system effects were associated with a Cmax value approximately 3-fold less than the Cmax in juvenile dogs, and 9-fold less than the Cmax in adult dogs following 28 days of dosing. At a dose of 25 mg/kg/day with associated Cmax and AUCinf values of 147 mcg/mL and 717 mcg∙h/mL, respectively (1.6 and 1.0-fold the adult human Cmax and AUC, respectively, at the 6 mg/kg/day dose), mild clinical signs of twitching and one incidence of muscle rigidity were observed with no corresponding effect on body weight. These effects were found to be reversible within 28 days after treatment had stopped.

At higher dose levels of 50 and 75 mg/kg/day with associated Cmax and AUCinf values of ≥321 mcg/mL and ≥1470 mcg∙h/mL, respectively, marked clinical signs of twitching, muscle rigidity in the limbs, and impaired use of limbs were observed. Resulting decreases in body weights and overall body condition at doses ≥50 mg/kg/day necessitated early discontinuation by postnatal day (PND) 19.

Histopathological assessment did not reveal any daptomycin-related changes in the peripheral and central nervous system tissue, as well as in the skeletal muscle or other tissues assessed, at any dose level.

No adverse effects were observed in the dogs that received daptomycin at 10 mg/kg/day, the NOAEL, with associated Cmax and AUCinf values of 62 mcg/mL and 247 mcg∙h/mL, respectively (or 0.6 and 0.4-fold the adult human Cmax and AUC, respectively at the 6 mg/kg dose).

14 CLINICAL STUDIES

14.1 Complicated Skin and Skin Structure Infections

Adults with cSSSI
Adult patients with clinically documented complicated skin and skin structure infections (cSSSI) (Table 16) were enrolled in two randomized, multinational, multicenter, investigator-blinded trials comparing daptomycin for injection (4 mg/kg IV every 24h) with either vancomycin (1 g IV q12h) or an anti-staphylococcal semi-synthetic penicillin (i.e., nafcillin, oxacillin, cloxacillin, or flucloxacillin; 4 to 12 g IV per day). Patients could switch to oral therapy after a minimum of 4 days of IV treatment if clinical improvement was demonstrated. Patients known to have bacteremia at baseline were excluded. Patients with creatinine clearance (CLCR) between 30 and 70 mL/min were to receive a lower dose of daptomycin for injection as specified in the protocol; however, the majority of patients in this subpopulation did not have the dose of daptomycin for injection adjusted.

Table 16: Investigator's Primary Diagnosis in the cSSSI Trials in Adult Patients (Population: ITT)

Primary Diagnosis | Adult Patients (Daptomycin for Injection / Comparator*)
Primary Diagnosis | Study 9801 N=264 / N=266 | Study 9901 N=270 / N=292 | Pooled N=534 / N=558
Wound Infection | 99 (38%) / 116 (44%) | 102 (38%) / 108 (37%) | 201 (38%) / 224 (40%)
Major Abscess | 55 (21%) / 43 (16%) | 59 (22%) / 65 (22%) | 114 (21%) / 108 (19%)
Ulcer Infection | 71 (27%) / 75 (28%) | 53 (20%) / 68 (23%) | 124 (23%) / 143 (26%)
Other Infection† | 39 (15%) / 32 (12%) | 56 (21%) / 51 (18%) | 95 (18%) / 83 (15%)

* Comparator: vancomycin (1 g IV q12h) or an anti-staphylococcal semi-synthetic penicillin (i.e., nafcillin, oxacillin, cloxacillin, or flucloxacillin; 4 to 12 g/day IV in divided doses).
† The majority of cases were subsequently categorized as complicated cellulitis, major abscesses, or traumatic wound infections.

One trial was conducted primarily in the United States and South Africa (study 9801), and the second was conducted at non-US sites only (study 9901). The two trials were similar in design but differed in patient characteristics, including history of diabetes and peripheral vascular disease. There were a total of 534 adult patients treated with daptomycin and 558 treated with comparator in the two trials. The majority (89.7%) of patients received IV medication exclusively.

The efficacy endpoints in both trials were the clinical success rates in the intent-to-treat (ITT) population and in the clinically evaluable (CE) population. In study 9801, clinical success rates in the ITT population were 62.5% (165/264) in patients treated with daptomycin for injection and 60.9% (162/266) in patients treated with comparator drugs. Clinical success rates in the CE population were 76.0% (158/208) in patients treated with daptomycin for injection and 76.7% (158/206) in patients treated with comparator drugs. In study 9901, clinical success rates in the ITT population were 80.4% (217/270) in patients treated with daptomycin and 80.5% (235/292) in patients treated with comparator drugs. Clinical success rates in the CE population were 89.9% (214/238) in patients treated with daptomycin for injection and 90.4% (226/250) in patients treated with comparator drugs.

The success rates by pathogen for microbiologically evaluable patients are presented in Table 17.

Table 17: Clinical Success Rates by Infecting Pathogen in the cSSSI Trials in Adult Patients (Population: Microbiologically Evaluable)

Pathogen | Success Rate n/N (%)
Pathogen | Daptomycin for Injection | Comparator*
Methicillin-susceptible Staphylococcus aureus (MSSA)† | 170/198 (86%) | 180/207 (87%)
Methicillin-resistant Staphylococcus aureus (MRSA)† | 21/28 (75%) | 25/36 (69%)
Streptococcus pyogenes | 79/84 (94%) | 80/88 (91%)
Streptococcus agalactiae | 23/27 (85%) | 22/29 (76%)
Streptococcus dysgalactiae subsp. equisimilis | 8/8 (100%) | 9/11 (82%)
Enterococcus faecalis (vancomycin- susceptible only) | 27/37 (73%) | 40/53 (76%)

* Comparator: vancomycin (1 g IV q12h) or an anti-staphylococcal semi-synthetic penicillin (i.e., nafcillin, oxacillin, cloxacillin, or flucloxacillin; 4 to 12 g/day IV in divided doses).
† As determined by the central laboratory.

Pediatric Patients (1 to 17 Years of Age) with cSSSI
The cSSSI pediatric trial was a single prospective multi-center, randomized, comparative trial. A total of 396 pediatric patients aged 1 to 17 years with cSSSI caused by Gram positive pathogens were enrolled into the study. Patients known to have bacteremia, osteomyelitis, endocarditis, and pneumonia at baseline were excluded. Patients were enrolled in a stepwise approach into four age groups and given age-dependent doses of daptomycin once daily for up to 14 days. The different age groups and doses evaluated were as follows: Adolescents (12 to 17 years) treated with 5 mg/kg of daptomycin (n=113), Children (7 to 11 years) treated with 7 mg/kg of daptomycin for injection (n=113), Children (2 to 6 years) treated with 9 mg/kg of daptomycin for injection (n=125) and Infants (1 to <2 years) treated with 10 mg/kg (n= 45).

Patients were randomized 2:1 to receive daptomycin for injection or a standard of care (SOC) comparator, which included intravenous therapy with either vancomycin, clindamycin, or an anti-staphylococcal semi-synthetic penicillin (nafcillin, oxacillin, or cloxacillin). Patients could switch to oral therapy after clinical improvement was demonstrated (no minimum IV dosing was required).

The primary objective of this study was to evaluate the safety of daptomycin for injection. The clinical outcome was determined by resolution or improvement of symptoms at the End-of-Treatment (EOT), 3 days after the last dose, and Test-of-Cure (TOC), 7 to 14 days after the last dose. Investigator observed outcomes were verified in a blinded fashion. Of the 396 subjects randomized in the study, 389 subjects were treated with daptomycin for injection or comparator and included in the ITT population. Of these, 257 subjects were randomized to the daptomycin for injection group and 132 subjects were randomized to the comparator group. Approximately 95% of subjects switched to oral therapy. The mean day of switch was day 4, and ranged from day 1 to day 14. The clinical success rates determined at 7 to 14 days after last dose of therapy (IV and oral) (TOC visit) were 88% (227/257) for daptomycin for injection and 86% (114/132) for comparator.

14.2 S. aureus Bacteremia/Endocarditis

Adults with S. aureus Bacteremia/Endocarditis
The efficacy of daptomycin for injection in the treatment of adult patients with S. aureus bacteremia was demonstrated in a randomized, controlled, multinational, multicenter, open-label trial. In this trial, adult patients with at least one positive blood culture for S. aureus obtained within 2 calendar days prior to the first dose of study drug and irrespective of source were enrolled and randomized to either daptomycin for injection (6 mg/kg IV every 24h) or standard of care [an anti-staphylococcal semi-synthetic penicillin 2 g IV q4h (nafcillin, oxacillin, cloxacillin, or flucloxacillin) or vancomycin 1 g IV q12h, each with initial gentamicin 1 mg/kg IV every 8 hours for first 4 days]. Of the patients in the comparator group, 93% received initial gentamicin for a median of 4 days, compared with 1 patient (<1%) in the daptomycin for injection group. Patients with prosthetic heart valves, intravascular foreign material that was not planned for removal within 4 days after the first dose of study medication, severe neutropenia, known osteomyelitis, polymicrobial bloodstream infections, creatinine clearance <30 mL/min, and pneumonia were excluded.

Upon entry, patients were classified for likelihood of endocarditis using the modified Duke criteria (Possible, Definite, or Not Endocarditis). Echocardiography, including a transesophageal echocardiogram (TEE), was performed within 5 days following study enrollment. The choice of comparator agent was based on the oxacillin susceptibility of the S. aureus isolate. The duration of study treatment was based on the investigator's clinical diagnosis. Final diagnoses and outcome assessments at Test of Cure (6 weeks after the last treatment dose) were made by a treatment-blinded Adjudication Committee, using protocol-specified clinical definitions and a composite primary efficacy endpoint (clinical and microbiological success) at the Test of Cure visit.

A total of 246 patients ≥18 years of age (124 daptomycin for injection, 122 comparator) with S. aureus bacteremia were randomized from 48 centers in the US and Europe. In the ITT population, 120 patients received daptomycin for injection and 115 received comparator (62 received an anti-staphylococcal semi-synthetic penicillin and 53 received vancomycin). Thirty-five patients treated with an anti-staphylococcal semi-synthetic penicillin received vancomycin initially for 1 to 3 days, pending final susceptibility results for the S. aureus isolates. The median age among the 235 patients in the ITT population was 53 years (range: 21 to 91 years); 30/120 (25%) in the daptomycin for injection group and 37/115 (32%) in the comparator group were ≥65 years of age. Of the 235 ITT patients, there were 141 (60%) males and 156 (66%) Caucasians across the two treatment groups. In addition, 176 (75%) of the ITT population had systemic inflammatory response syndrome (SIRS) at baseline and 85 (36%) had surgical procedures within 30 days prior to onset of the S. aureus bacteremia. Eighty-nine patients (38%) had bacteremia caused by methicillin-resistant S. aureus (MRSA). Entry diagnosis was based on the modified Duke criteria and comprised 37 (16%) Definite, 144 (61%) Possible, and 54 (23%) Not Endocarditis. Of the 37 patients with an entry diagnosis of Definite Endocarditis, all (100%) had a final diagnosis of infective endocarditis, and of the 144 patients with an entry diagnosis of Possible Endocarditis, 15 (10%) had a final diagnosis of infective endocarditis as assessed by the Adjudication Committee. Of the 54 patients with an entry diagnosis of Not Endocarditis, 1 (2%) had a final diagnosis of infective endocarditis as assessed by the Adjudication Committee.

In the ITT population, there were 182 patients with bacteremia and 53 patients with infective endocarditis as assessed by the Adjudication Committee, including 35 with right-sided endocarditis and 18 with left-sided endocarditis. The 182 patients with bacteremia comprised 121 with complicated S. aureus bacteremia and 61 with uncomplicated S. aureus bacteremia.

Complicated bacteremia was defined as S. aureus isolated from blood cultures obtained on at least 2 different calendar days, and/or metastatic foci of infection (deep tissue involvement), and classification of the patient as not having endocarditis according to the modified Duke criteria. Uncomplicated bacteremia was defined as S. aureus isolated from blood culture(s) obtained on a single calendar day, no metastatic foci of infection, no infection of prosthetic material, and classification of the patient as not having endocarditis according to the modified Duke criteria. The definition of right-sided infective endocarditis (RIE) used in the clinical trial was Definite or Possible Endocarditis according to the modified Duke criteria and no echocardiographic evidence of predisposing pathology or active involvement of either the mitral or aortic valve. Complicated RIE comprised patients who were not intravenous drug users, had a positive blood culture for MRSA, serum creatinine ≥2.5 mg/dL, or evidence of extrapulmonary sites of infection. Patients who were intravenous drug users, had a positive blood culture for methicillin-susceptible S. aureus (MSSA), had serum creatinine <2.5 mg/dL, and were without evidence of extrapulmonary sites of infection were considered to have uncomplicated RIE.

The coprimary efficacy endpoints in the trial were the Adjudication Committee success rates at the Test of Cure visit (6 weeks after the last treatment dose) in the ITT and Per Protocol (PP) populations. The overall Adjudication Committee success rates in the ITT population were 44.2% (53/120) in patients treated with daptomycin for injection and 41.7% (48/115) in patients treated with comparator (difference = 2.4% [95% CI −10.2, 15.1]). The success rates in the PP population were 54.4% (43/79) in patients treated with daptomycin and 53.3% (32/60) in patients treated with comparator (difference = 1.1% [95% CI −15.6, 17.8]).

Adjudication Committee success rates are shown in Table 18.

Table 18: Adjudication Committee Success Rates at Test of Cure in the S. aureus Bacteremia/Endocarditis Trial in Adult Patients (Population: ITT)

Population | Success Rate n/N (%) |  | Difference: Daptomycin for Injection−Comparator (Confidence Interval)
Population | Daptomycin for Injection 6 mg/kg | Comparator* | Difference: Daptomycin for Injection−Comparator (Confidence Interval)
Overall | 53/120 (44%) | 48/115 (42%) | 2.4% (−10.2, 15.1)†
Baseline Pathogen
Methicillin- susceptible S. aureus | 33/74 (45%) | 34/70 (49%) | −4.0% (−22.6, 14.6)‡
Methicillin-resistant S. aureus | 20/45 (44%) | 14/44 (32%) | 12.6% (−10.2, 35.5)‡
Entry Diagnosis§
Definite or Possible Infective Endocarditis | 41/90 (46%) | 37/91 (41%) | 4.9% (−11.6, 21.4)‡
Not Infective Endocarditis | 12/30 (40%) | 11/24 (46%) | −5.8% (−36.2, 24.5)‡
Final Diagnosis
Uncomplicated Bacteremia | 18/32 (56%) | 16/29 (55%) | 1.1% (−31.7, 33.9)¶
Complicated Bacteremia | 26/60 (43%) | 23/61 (38%) | 5.6% (−17.3, 28.6)¶
Right-Sided Infective Endocarditis | 8/19 (42%) | 7/16 (44%) | −1.6% (−44.9, 41.6)¶
Uncomplicated Right-Sided Infective Endocarditis | 3/6 (50%) | 1/4 (25%) | 25.0% (−51.6, 100.0)¶
Complicated Right-Sided Infective Endocarditis | 5/13 (39%) | 6/12 (50%) | −11.5% (−62.4, 39.4)¶
Left-Sided Infective Endocarditis | 1/9 (11%) | 2/9 (22%) | −11.1% (−55.9, 33.6)¶

* Comparator: vancomycin (1 g IV q12h) or an anti-staphylococcal semi-synthetic penicillin (i.e., nafcillin, oxacillin, cloxacillin, or flucloxacillin; 2 g IV q4h), each with initial low-dose gentamicin.
† 95% Confidence Interval
‡ 97.5% Confidence Interval (adjusted for multiplicity)
§ According to the modified Duke criteria^5

¶ 99% Confidence Interval (adjusted for multiplicity)

Eighteen (18/120) patients in the daptomycin for injection arm and 19/116 patients in the comparator arm died during the trial. These comprise 3/28 daptomycin-treated patients and 8/26 comparator-treated patients with endocarditis, as well as 15/92 daptomycin-treated patients and 11/90 comparator-treated patients with bacteremia. Among patients with persisting or relapsing S. aureus infections, 8/19 daptomycin-treated patients and 7/11 comparator-treated patients died.

Overall, there was no difference in time to clearance of S. aureus bacteremia between daptomycin and comparator. The median time to clearance in patients with MSSA was 4 days and in patients with MRSA was 8 days.

Failure of treatment due to persisting or relapsing S. aureus infections was assessed by the Adjudication Committee in 19/120 (16%) daptomycin-treated patients (12 with MRSA and 7 with MSSA) and 11/115 (10%) comparator-treated patients (9 with MRSA treated with vancomycin and 2 with MSSA treated with an anti-staphylococcal semi-synthetic penicillin). Among all failures, isolates from 6 daptomycin-treated patients and 1 vancomycin-treated patient developed increasing MICs (reduced susceptibility) by central laboratory testing during or following therapy. Most patients who failed due to persisting or relapsing S. aureus infection had deep-seated infection and did not receive necessary surgical intervention [see Warnings and Precautions (5.9)].

Pediatric Patients (1 to 17 Years of Age) with S. aureus Bacteremia
The pediatric S. aureus bacteremia study was designed as a prospective multi-center, randomized, comparative trial to treat pediatric patients aged 1 to 17 years with bacteremia. Patients known to have endocarditis or pneumonia at baseline were excluded. Patients were enrolled in a stepwise approach into three age groups and given age-dependent doses of daptomycin once daily for up to 42 days. The different age groups and doses evaluated were as follows: Adolescents (12 to 17 years, n=14 patients) treated with daptomycin dosed at 7 mg/kg once daily, Children (7 to 11 years, n=19 patients) treated with daptomycin dosed at 9 mg/kg once daily and Children (2 to 6 years, n=22 patients) treated with daptomycin dosed at 12 mg/kg once daily. No patients 1 to <2 years of age were enrolled.

Patients were randomized 2:1 to receive daptomycin or a standard of care comparator, which included intravenous therapy with vancomycin, semi-synthetic penicillin, first generation cephalosporin or clindamycin. Patients could switch to oral therapy after clinical improvement was demonstrated (no minimum IV dosing was required).

The primary objective of this study was to assess the safety of daptomycin. The clinical outcome was determined by resolution or improvement of symptoms at test-of-cure (TOC) visit, 7 to 14 days after the last dose, which was assessed by the site level Blinded Evaluator.

Of the 82 subjects randomized in the study, 81 subjects were treated with daptomycin for injection or comparator and included in the safety population, and 73 had a proven S. aureus bacteremia at Baseline. Of these, 51 subjects were randomized to the daptomycin for injection group and 22 subjects were randomized to the comparator group. The mean duration of IV therapy was 12 days, with a range of 1 to 44 days. Forty-eight subjects switched to oral therapy, and the mean duration of oral therapy was 21 days. The clinical success rates determined at 7 to 14 days after last dose of therapy (IV and oral) (TOC visit) were 88% (45/51) for daptomycin for injection and 77% (17/22) for comparator.

15 REFERENCES

1. Liu SL, Howard LC, Van Lier RBL, Markham JK: Teratology studies with daptomycin administered intravenously (iv) to rats and rabbits. Teratology 37(5):475, 1988.
2. Stroup JS, Wagner J, Badzinski T: Use of daptomycin in a pregnant patient with Staphylococcus aureus endocarditis. Ann Pharmacother 44(4):746-749, 2010.
3. Buitrago MI, Crompton JA, Bertolami S, North DS, Nathan RA. Extremely low excretion of daptomycin into breast milk of a nursing mother with methicillin-resistant Staphylococcus aureus pelvic inflammatory disease. Pharmacotherapy 2009;29(3):347–351.
4. Klibanov OM, Vickery S, Nortey C: Successful treatment of infective panniculitis with daptomycin in a pregnant, morbidly obese patient. Ann Pharmacother 48(5):652-655, 2014.
5. Li JS, Sexton DJ, Mick N, Nettles R, Fowler VG Jr, Ryan T, Bashore T, Corey GR. Proposed modifications to the Duke criteria for the diagnosis of infective endocarditis. Clin Infect Dis 2000;30:633–638.

16 HOW SUPPLIED/STORAGE AND HANDLING

Daptomycin for Injection is supplied as a sterile pale yellow to light brown lyophilized powder in single-dose vials containing 350 mg or 500 mg of daptomycin:

500 mg/vial - Package of 10 vials (NDC 42023-295-10)

Store original packages at 20°C to 25°C (68°F to 77°F); excursions permitted to 15°C to 30°C (59°F to 86°F) [see USP Controlled Room Temperature]. Storage conditions for the reconstituted and diluted solutions are described in another section of the prescribing information [see Dosage and Administration (2.7)].

17 PATIENT COUNSELING INFORMATION

Allergic Reactions
Advise patients that allergic reactions, including serious skin, kidney, lung, or other organ reactions, could occur and that these serious reactions require immediate treatment. Patients should report any previous allergic reactions to daptomycin [see Warnings and Precautions (5.1, 5.4, 5.5)].

Muscle Pain or Weakness (Myopathy and Rhabdomyolysis, Peripheral Neuropathy)
Advise patients to report muscle pain or weakness, especially in the forearms and lower legs, as well as tingling or numbness [see Warnings and Precautions (5.2, 5.6)].

Cough, Breathlessness, or Fever (Eosinophilic Pneumonia)
Advise patients to report any symptoms of cough, breathlessness, or fever [see Warnings and Precautions (5.3)].

C. difficile-Associated Diarrhea (CDAD)
Advise patients that diarrhea is a common problem caused by antibacterials including Daptomycin for Injection, that usually ends when the antibacterial is discontinued. Sometimes after starting treatment with antibacterials, including Daptomycin for Injection, patients can develop watery and bloody stools (with or without stomach cramps and fever), even as late as 2 or more months after having received the last dose of the antibacterial. If this occurs, patients should contact their physician as soon as possible [see Warnings and Precautions (5.8)].

Antibacterial Resistance
Patients should be counseled that antibacterial drugs, including Daptomycin for Injection, should be used to treat bacterial infections. They do not treat viral infections (e.g., the common cold). When Daptomycin for Injection is prescribed to treat a bacterial infection, patients should be told that although it is common to feel better early in the course of therapy, the medication should be administered exactly as directed. Skipping doses or not completing the full course of therapy may (1) decrease the effectiveness of the immediate treatment and (2) increase the likelihood that bacteria will develop resistance and will not be treatable by Daptomycin for Injection or other antibacterial drugs in the future.

Manufactured for:
Endo USA
Malvern, PA 19355

Made in India

PACKAGE LABEL.PRINCIPAL DISPLAY PANEL

NDC 42023-295-01 Rx only

DAPTOMYCIN
FOR INJECTION
500 mg per vial
Must Be Reconstituted
For Intravenous Use Only
Single-Dose Vial

NDC 42023-295-10 Rx only

DAPTOMYCIN
FOR INJECTION
500 mg per vial
Must Be Reconstituted
Use Sterile Water for Injection for Reconstitution
For Intravenous Use Only

Contains Ten Single-Dose Vials

Discard Unused Portion